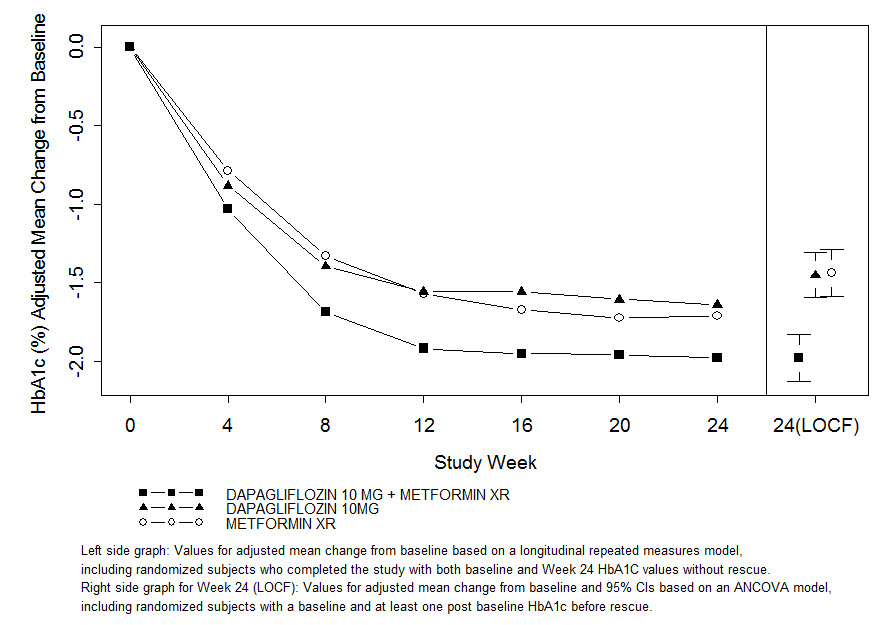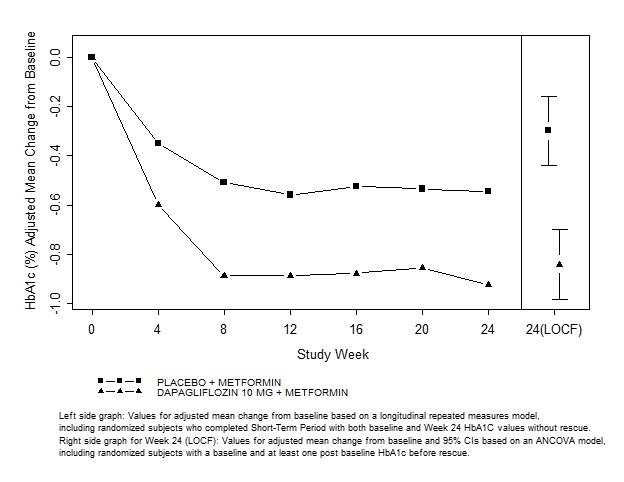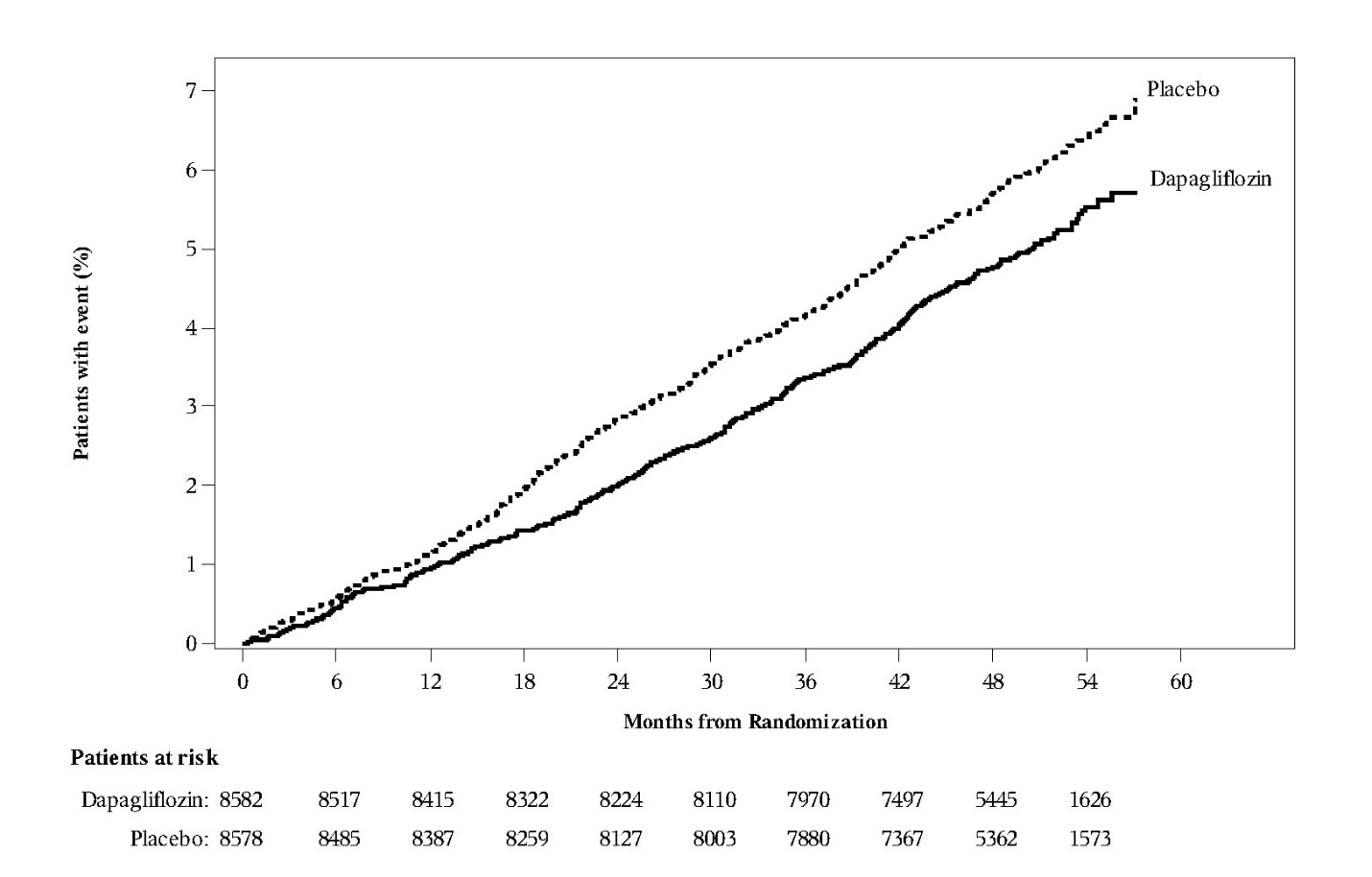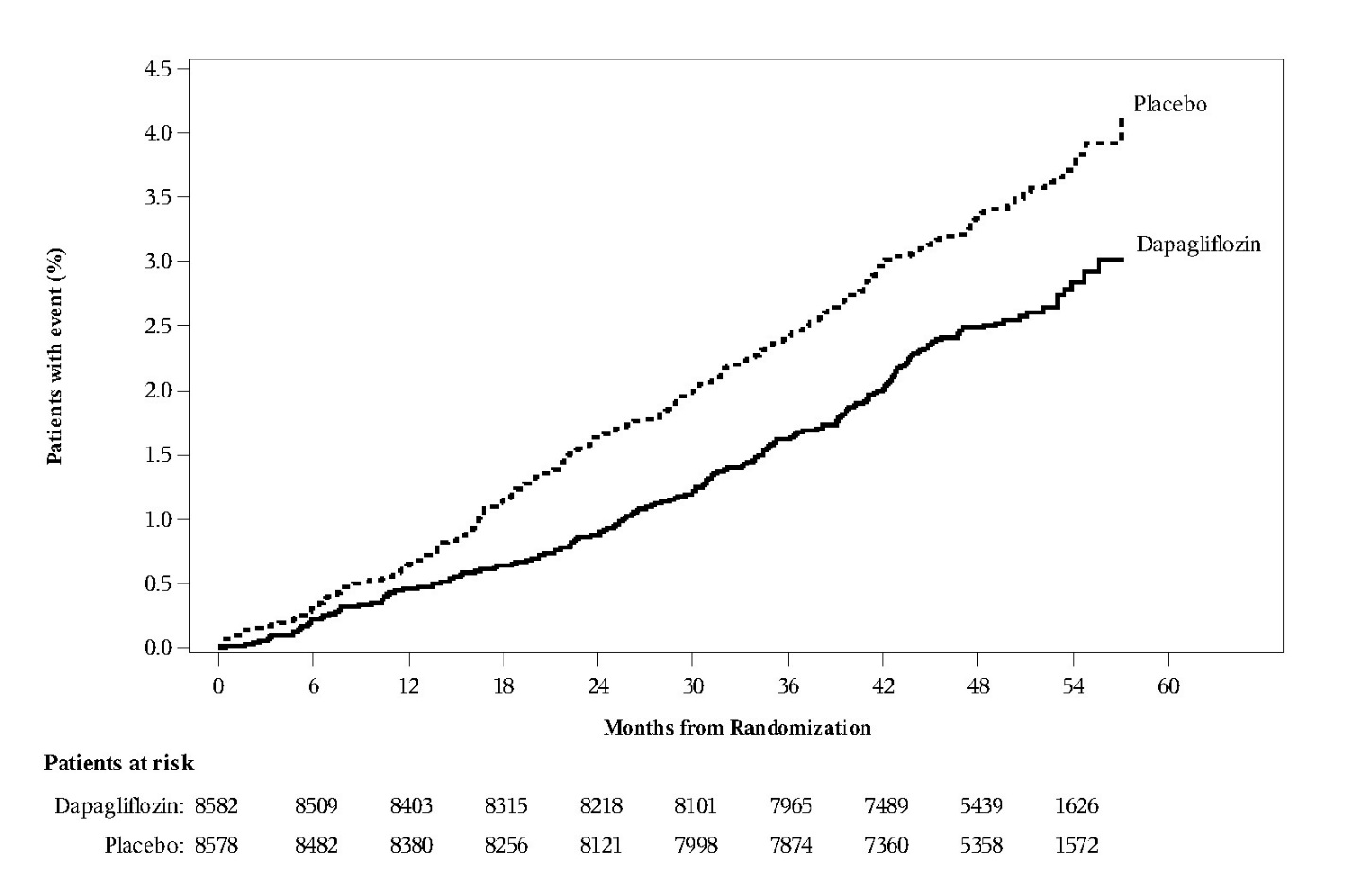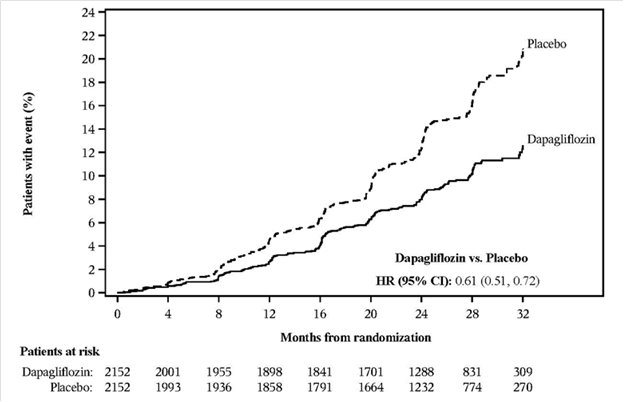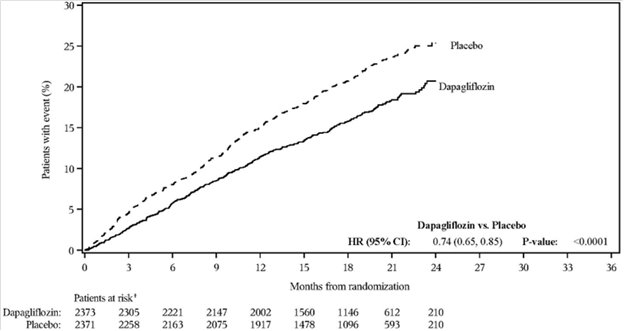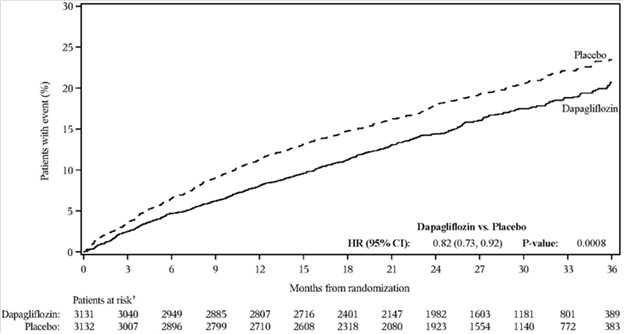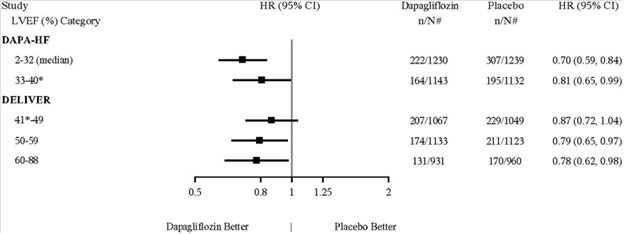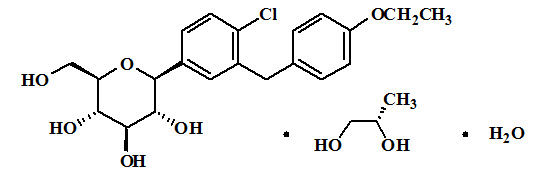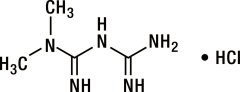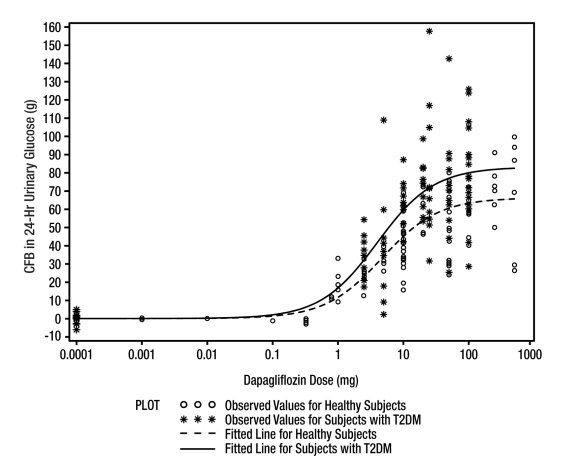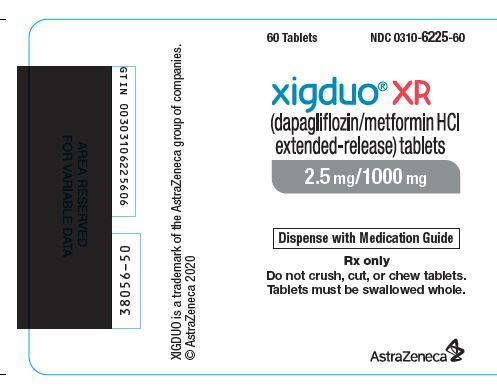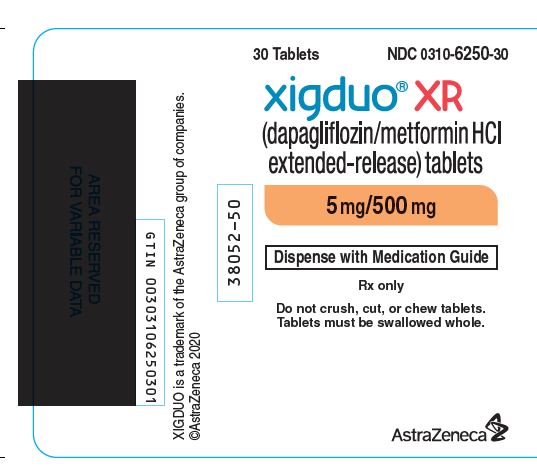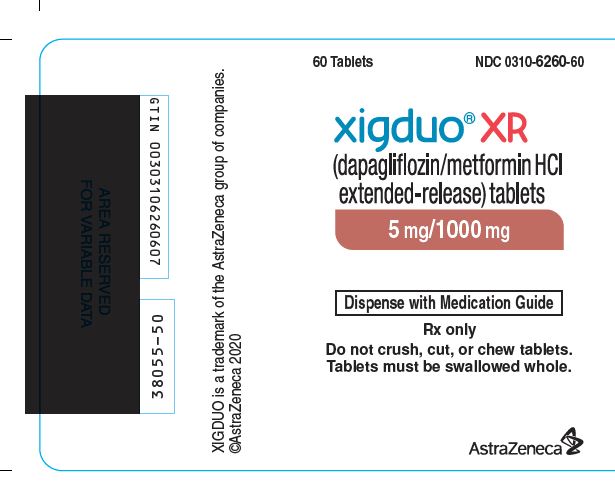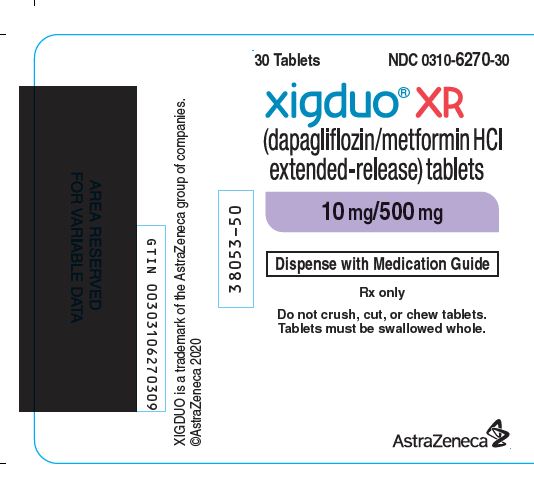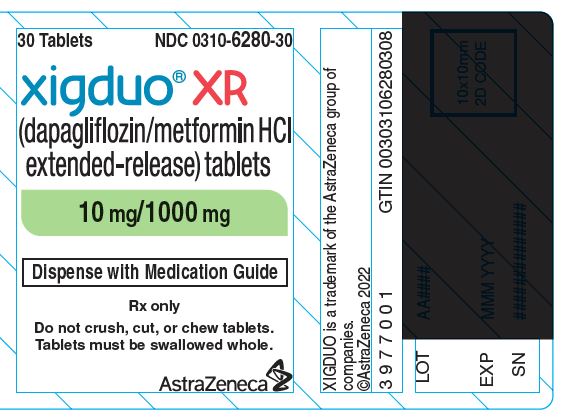 DRUG LABEL: XIGDUO
NDC: 0310-6270 | Form: TABLET, FILM COATED, EXTENDED RELEASE
Manufacturer: AstraZeneca Pharmaceuticals LP
Category: prescription | Type: HUMAN PRESCRIPTION DRUG LABEL
Date: 20241220

ACTIVE INGREDIENTS: DAPAGLIFLOZIN PROPANEDIOL 10 mg/1 1; METFORMIN HYDROCHLORIDE 500 mg/1 1
INACTIVE INGREDIENTS: anhydrous lactose; CARBOXYMETHYLCELLULOSE SODIUM, UNSPECIFIED; CROSPOVIDONE, UNSPECIFIED; HYPROMELLOSE 2208 (100000 MPA.S); magnesium stearate; MICROCRYSTALLINE CELLULOSE; silicon dioxide

HIGHLIGHTS OF PRESCRIBING INFORMATION

These highlights do not include all the information needed to use XIGDUO XR safely and effectively. See full prescribing information for XIGDUO XR.
XIGDUO® XR (dapagliflozin and metformin hydrochloride extended-release) tablets, for oral use
Initial U.S. Approval: 2014

RECENT MAJOR CHANGES

Indications and Usage (1) 12/2024

Dosage and Administration (2.3) 06/2024

WARNING: LACTIC ACIDOSIS

See full prescribing information for complete boxed warning.

- Postmarketing cases of metformin-associated lactic acidosis have resulted in death, hypothermia, hypotension, and resistant bradyarrhythmias. Symptoms included malaise, myalgias, respiratory distress, somnolence, and abdominal pain. Laboratory abnormalities included elevated blood lactate levels, anion gap acidosis, increased lactate/pyruvate ratio; and metformin plasma levels generally >5 mcg/mL. (5.1)
- Risk factors include renal impairment, concomitant use of certain drugs, age >65 years old, radiological studies with contrast, surgery and other procedures, hypoxic states, excessive alcohol intake, and hepatic impairment. Steps to reduce the risk of and manage metformin-associated lactic acidosis in these high-risk groups are provided in the Full Prescribing Information. (5.1)
- If lactic acidosis is suspected, discontinue XIGDUO XR and institute general supportive measures in a hospital setting. Prompt hemodialysis is recommended. (5.1)

1 INDICATIONS AND USAGE

XIGDUO XR is a combination of dapagliflozin, a sodium-glucose cotransporter 2 (SGLT2) inhibitor, and metformin hydrochloride (HCl), a biguanide, indicated as an adjunct to diet and exercise to improve glycemic control in adults and pediatric patients aged 10 years and older with type 2 diabetes mellitus. (1)

Dapagliflozin when used as a component of XIGDUO XR, is indicated in adults with type 2 diabetes mellitus to reduce the risk of:

- Sustained eGFR decline, end-stage kidney disease, cardiovascular death, and hospitalization for heart failure in patients with chronic kidney disease at risk of progression. (1)
- Cardiovascular death, hospitalization for heart failure, and urgent heart failure visit in patients with heart failure. (1)
- Hospitalization for heart failure in patients with type 2 diabetes mellitus and either established cardiovascular disease or multiple cardiovascular risk factors. (1)

Limitations of use:

- Not recommended for use to improve glycemic control in patients with type 1 diabetes mellitus. (1)
- Because of the metformin HCl component, the use of XIGDUO XR is limited to patients with type 2 diabetes mellitus for all indications. (1)
- Not recommended for the treatment of chronic kidney disease in patients with polycystic kidney disease or patients requiring or with a recent history of immunosuppressive therapy for the treatment of kidney disease. XIGDUO XR is not expected to be effective in these populations. (1)

2 DOSAGE AND ADMINISTRATION

- Assess renal function prior to initiating and then as clinically indicated. (2.1)
- Assess volume status and correct volume depletion before initiating. (2.1)
- Individualize the starting dosage based on the patient’s current treatment. (2.3)
- Administer orally once daily in the morning with food. (2.2)
- To improve glycemic control, for patients aged 10 years and older not already taking dapagliflozin, the recommended starting dosage for dapagliflozin is 5 mg once daily. (2.3)
- For indications in adults related to heart failure and chronic kidney disease the recommended dosage of dapagliflozin is 10 mg once daily. (2.3)
- Do not exceed a daily dosage of 10 mg dapagliflozin/2,000 mg metformin HCl extended-release. (2.3)
- See Full Prescribing Information for dosage recommendations in patients with renal impairment. (2.4)
- XIGDUO XR may need to be discontinued at time of, or prior to, iodinated contrast imaging procedures. (2.5)
- Withhold XIGDUO XR for at least 3 days, if possible, prior to surgery or procedures associated with prolonged fasting. (2.6)

3 DOSAGE FORMS AND STRENGTHS

- 2.5 mg dapagliflozin/1,000 mg metformin HCl extended-release (3)
- 5 mg dapagliflozin/500 mg metformin HCl extended-release (3)
- 5 mg dapagliflozin/1,000 mg metformin HCl extended-release (3)
- 10 mg dapagliflozin/500 mg metformin HCl extended-release (3)
- 10 mg dapagliflozin/1,000 mg metformin HCl extended-release (3)

4 CONTRAINDICATIONS

- Severe renal impairment (eGFR below 30 mL/min/1.73 m^2) or end-stage renal disease. (4)
- History of serious hypersensitivity to dapagliflozin, metformin HCl, or any of the excipients in XIGDUO XR. (4)
- Metabolic acidosis, including diabetic ketoacidosis. (4)

5 WARNINGS AND PRECAUTIONS

- Lactic Acidosis: See boxed warning. (5.1)
- Diabetic Ketoacidosis in Patients with Type 1 Diabetes Mellitus and Other Ketoacidosis: Consider ketone monitoring in patients at risk for ketoacidosis, as indicated. Assess for ketoacidosis regardless of presenting blood glucose levels and discontinue XIGDUO XR if ketoacidosis is suspected. Monitor patients for resolution of ketoacidosis before restarting. (5.2)
- Volume Depletion: Before initiating XIGDUO XR, assess and correct volume status in the elderly, patients with renal impairment or low systolic blood pressure, and in patients on diuretics. Monitor for signs and symptoms during therapy. (5.3)
- Urosepsis and Pyelonephritis: Evaluate patients for signs and symptoms of urinary tract infections and treat promptly, if indicated. (5.4)
- Hypoglycemia: Consider a lower dosage of insulin or an insulin secretagogue to reduce the risk of hypoglycemia when used concomitantly with XIGDUO XR. (5.5)
- Necrotizing Fasciitis of the Perineum (Fournier’s Gangrene): Serious, life-threatening cases have occurred in both females and males. Assess patients presenting with pain or tenderness, erythema, or swelling in the genital or perineal area, along with fever or malaise. If suspected, institute prompt treatment. (5.6)
- Vitamin B12 Deficiency: Metformin may lower vitamin B12 levels. Measure hematological parameters annually. (5.7)
- Genital Mycotic Infections: Monitor and treat if indicated. (5.8)

6 ADVERSE REACTIONS

- Adverse reactions reported in >5% of patients treated with XIGDUO XR were female genital mycotic infection, nasopharyngitis, urinary tract infection, diarrhea, and headache. (6.1)
- Adverse reactions reported in >5% of patients treated with metformin extended-release are: diarrhea and nausea/vomiting. (6.1)

To report SUSPECTED ADVERSE REACTIONS, contact AstraZeneca at 1-800-236-9933 or FDA at 1-800-FDA-1088 or www.fda.gov/medwatch.

7 DRUG INTERACTIONS

- Carbonic anhydrase inhibitors: May increase risk of lactic acidosis. Consider more frequent monitoring. (7)
- Drugs that reduce metformin clearance: May increase risk of lactic acidosis. Consider benefits and risks of concomitant use. (7)
- See full prescribing information for additional drug interactions and information on interference of XIGDUO XR with laboratory tests. (7)

8 USE IN SPECIFIC POPULATIONS

- Pregnancy: Advise females of the potential risk to a fetus, especially during the second and third trimesters. (8.1)
- Lactation: Not recommended when breastfeeding. (8.2)
- Females and Males of Reproductive Potential: Advise premenopausal females of the potential for an unintended pregnancy. (8.3)
- Geriatrics: Higher incidence of adverse reactions related to hypotension. Assess renal function more frequently. (8.5, 8.6)
- Renal Impairment: Higher incidence of adverse reactions related to volume depletion. (8.6)
- Hepatic Impairment: Avoid use in patients with hepatic impairment. (8.7)

FULL PRESCRIBING INFORMATION

WARNING: LACTIC ACIDOSIS

• Postmarketing cases of metformin-associated lactic acidosis have resulted in death, hypothermia, hypotension, and resistant bradyarrhythmias. The onset of metformin-associated lactic acidosis is often subtle, accompanied only by non‑specific symptoms such as malaise, myalgias, respiratory distress, somnolence, and abdominal pain. Metformin-associated lactic acidosis was characterized by elevated blood lactate levels (>5 mmol/L), anion gap acidosis (without evidence of ketonuria or ketonemia), an increased lactate/pyruvate ratio; and metformin plasma levels generally >5 mcg/mL [see Warnings and Precautions (5.1)].

• Risk factors for metformin-associated lactic acidosis include renal impairment, concomitant use of certain drugs (e.g., carbonic anhydrase inhibitors such as topiramate), age 65 years old or greater, having a radiological study with contrast, surgery and other procedures, hypoxic states (e.g., acute congestive heart failure), excessive alcohol intake, and hepatic impairment.

• Steps to reduce the risk of and manage metformin-associated lactic acidosis in these high-risk groups are provided in the full prescribing information [see Dosage and Administration (2.1 and 2.4), Contraindications (4), Warnings and Precautions (5.1), Drug Interactions (7), and Use in Specific Populations (8.6, 8.7)].

• If metformin-associated lactic acidosis is suspected, immediately discontinue XIGDUO XR and institute general supportive measures in a hospital setting. Prompt hemodialysis is recommended [see Warnings and Precautions (5.1)].

1 INDICATIONS AND USAGE

XIGDUO XR is a combination of dapagliflozin and metformin hydrochloride (HCl) extended-release, indicated as an adjunct to diet and exercise to improve glycemic control in adults and pediatric patients aged 10 years and older with type 2 diabetes mellitus.

Dapagliflozin, when used as a component of XIGDUO XR, is indicated in adults with type 2 diabetes mellitus to reduce the risk of:

- Sustained eGFR decline, end‑stage kidney disease, cardiovascular death, and hospitalization for heart failure in patients with chronic kidney disease at risk of progression.
- Cardiovascular death, hospitalization for heart failure, and urgent heart failure visit in patients with heart failure.
- Hospitalization for heart failure in patients with type 2 diabetes mellitus and either established cardiovascular disease (CVD) or multiple cardiovascular (CV) risk factors.

Limitations of Use

- XIGDUO XR is not recommended for use to improve glycemic control in patients with type 1 diabetes mellitus [see Warnings and Precautions (5.2)].
- Because of the metformin HCl component, the use of XIGDUO XR is limited to patients with type 2 diabetes mellitus for all indications.
- XIGDUO XR is not recommended for the treatment of chronic kidney disease in patients with polycystic kidney disease or patients requiring or with a recent history of immunosuppressive therapy for kidney disease. XIGDUO XR is not expected to be effective in these populations.

2 DOSAGE AND ADMINISTRATION

2.1 Testing Prior to Initiation of XIGDUO XR

- Assess renal function prior to initiating XIGDUO XR and then as clinically indicated [see Warnings and Precautions (5.1, 5.3)].
- Assess volume status. In patients with volume depletion, correct this condition before initiating XIGDUO XR [see Warnings and Precautions (5.3) and Use in Specific Populations (8.5, 8.6)].

2.2 Recommended Administration

- Take XIGDUO XR orally once daily in the morning with food.
- Swallow XIGDUO XR tablets whole and never crush, cut, or chew.

2.3 Recommended Dosage

- Individualize the starting dosage of XIGDUO XR based upon the patient’s current regimen. Patients taking an evening dosage of metformin HCl extended‑release should skip their last dose before starting XIGDUO XR.
- To improve glycemic control in adults and pediatric patients aged 10 years and older not already taking:
  ∘ Dapagliflozin: the recommended starting dosage of dapagliflozin in XIGDUO XR is 5 mg orally once daily.
  ∘ Metformin HCl extended‑release: the recommended starting dosage of metformin HCl extended‑release in XIGDUO XR is 500 mg orally once daily.
- For XIGDUO XR indications in adults related to heart failure and chronic kidney disease, the recommended dosage of dapagliflozin in XIGDUO XR is 10 mg orally once daily.
- For all XIGDUO XR indications, the dosage may be adjusted based on effectiveness and tolerability. The maximum recommended daily dosage of dapagliflozin is 10 mg and 2,000 mg of metformin HCl extended‑release, with gradual dosage escalation to reduce gastrointestinal adverse reactions with metformin HCl [see Adverse Reactions (6.1)].

2.4 Recommended Dosage in Patients with Renal Impairment

- The recommended dosage of XIGDUO XR in patients with an estimated glomerular filtration rate (eGFR) greater than or equal to 45 mL/min/1.73 m^2 is the same as the recommended dosage in patients with normal renal function.
- Initiation of XIGDUO XR is not recommended in patients with an eGFR between 30 and 45 mL/min/1.73 m^2. Assess the benefit and risk of continuing therapy if eGFR falls persistently below this level.
  ∘ Dapagliflozin is likely to be ineffective to improve glycemic control in patients with eGFR less than 45 mL/min/1.73 m^2.
  ∘ Metformin HCl initiation is not recommended for patients with eGFR less than 45 mL/min/1.73 m^2.
- XIGDUO XR is contraindicated in patients with an eGFR below 30 mL/min/1.73 m2 and end‑stage renal disease due to the metformin HCl component [see Contraindications (4), Warnings and Precautions (5.1, 5.2), and Use in Specific Populations (8.6)].

2.5 Discontinuation for Iodinated Contrast Imaging Procedures

Discontinue XIGDUO XR at the time of, or prior to, an iodinated contrast imaging procedure in patients with an eGFR less than 60 mL/min/1.73 m^2, in patients with a history of liver disease, alcoholism or heart failure; or in patients who will be administered intra-arterial iodinated contrast. Re-evaluate eGFR 48 hours after the imaging procedure; restart XIGDUO XR if renal function is stable [see Warnings and Precautions (5.1)].

2.6 Temporary Interruption for Surgery

Withhold XIGDUO XR for at least 3 days, if possible, prior to surgery or procedures associated with prolonged fasting. Resume XIGDUO XR when the patient is clinically stable and has resumed oral intake [see Warnings and Precautions (5.2) and Clinical Pharmacology (12.2)].

3 DOSAGE FORMS AND STRENGTHS

XIGDUO XR (dapagliflozin and metformin HCl) extended-release tablets are available as follows:

Table 1: Dosage Forms and Strengths for XIGDUO XR
Dapagliflozin Strength | Metformin HCl Strength | Color/Shape | Tablet Markings
2.5 mg | 1,000 mg | light brown to brown, biconvex, oval-shaped, and film-coated tablet | "1074" and "2.5/1000" debossed on one side and plain on the reverse side
5 mg | 500 mg | orange, biconvex, capsule-shaped, and film-coated tablet | "1070" and "5/500" debossed on one side and plain on the reverse side
5 mg | 1,000 mg | pink to dark pink, biconvex, oval-shaped, and film-coated tablet | "1071" and "5/1000" debossed on one side and plain on the reverse side
10 mg | 500 mg | pink, biconvex, capsule-shaped, and film-coated tablet | "1072" and "10/500" debossed on one side and plain on the reverse side
10 mg | 1,000 mg | yellow to dark yellow, biconvex, oval-shaped, and film-coated tablet | "1073" and "10/1000" debossed on one side and plain on the reverse side

4 CONTRAINDICATIONS

XIGDUO XR is contraindicated in patients with:

- Severe renal impairment (eGFR below 30 mL/min/1.73 m^2) or end-stage renal disease [see Warnings and Precautions (5.1)].
- History of a serious hypersensitivity reaction to dapagliflozin, metformin HCl, or any of the excipients in XIGDUO XR. Serious hypersensitivity reactions, including anaphylaxis and angioedema have been reported with dapagliflozin [see Adverse Reactions (6.1)].
- Acute or chronic metabolic acidosis, including diabetic ketoacidosis, with or without coma. Diabetic ketoacidosis should be treated with insulin [see Warnings and Precautions (5.1) and Warnings and Precautions (5.2)].

5 WARNINGS AND PRECAUTIONS

5.1 Lactic Acidosis

There have been post-marketing cases of metformin-associated lactic acidosis, including fatal cases. These cases had a subtle onset and were accompanied by non‑specific symptoms such as malaise, myalgias, abdominal pain, respiratory distress, or increased somnolence; however, hypothermia, hypotension and resistant bradyarrhythmias have occurred with severe acidosis.

Metformin-associated lactic acidosis was characterized by elevated blood lactate concentrations (>5 mmol/L), anion gap acidosis (without evidence of ketonuria or ketonemia), and an increased lactate: pyruvate ratio; metformin plasma levels generally >5 mcg/mL. Metformin decreases liver uptake of lactate increasing lactate blood levels which may increase the risk of lactic acidosis, especially in patients at risk.

If metformin-associated lactic acidosis is suspected, general supportive measures should be instituted promptly in a hospital setting, along with immediate discontinuation of XIGDUO XR.

In XIGDUO XR-treated patients with a diagnosis or strong suspicion of lactic acidosis, prompt hemodialysis is recommended to correct the acidosis and remove accumulated metformin (metformin HCl is dialyzable, with a clearance of up to 170 mL/min under good hemodynamic conditions). Hemodialysis has often resulted in reversal of symptoms and recovery.

Educate patients and their families about the symptoms of lactic acidosis and if these symptoms occur, instruct them to discontinue XIGDUO XR and report these symptoms to their healthcare provider.

For each of the known and possible risk factors for metformin-associated lactic acidosis, recommendations to reduce the risk of and manage metformin-associated lactic acidosis are provided below:

Renal Impairment: The postmarketing metformin-associated lactic acidosis cases primarily occurred in patients with significant renal impairment. The risk of metformin accumulation and metformin-associated lactic acidosis increases with the severity of renal impairment because metformin is substantially excreted by the kidney. Clinical recommendations based upon the patient’s renal function include [see Dosage and Administration (2.1, 2.4) and Clinical Pharmacology (12.3)]:

- Before initiating XIGDUO XR, obtain an estimated glomerular filtration rate (eGFR).
- XIGDUO XR is contraindicated in patients with an eGFR less than 30 mL/min/1.73 m^2 [see Contraindications (4)].
- Obtain an eGFR at least annually in all patients taking XIGDUO XR. In patients at increased risk for the development of renal impairment (e.g., the elderly), renal function should be assessed more frequently.

Drug Interactions: The concomitant use of XIGDUO XR with specific drugs may increase the risk of metformin-associated lactic acidosis: those that impair renal function, result in significant hemodynamic change, interfere with acid-base balance or increase metformin accumulation (e.g., cationic drugs) [see Drug Interactions (7)]. Therefore, consider more frequent monitoring of patients.

Age 65 or Greater: The risk of metformin-associated lactic acidosis increases with the patient’s age because elderly patients have a greater likelihood of having hepatic, renal, or cardiac impairment than younger patients. Assess renal function more frequently in elderly patients [see Use in Specific Populations (8.5)].

Radiological Studies with Contrast: Administration of intravascular iodinated contrast agents in metformin-treated patients has led to an acute decrease in renal function and the occurrence of lactic acidosis. Stop XIGDUO XR at the time of, or prior to, an iodinated contrast imaging procedure in patients with a history of hepatic impairment, alcoholism, or heart failure; or in patients who will be administered intra-arterial iodinated contrast. Re-evaluate eGFR 48 hours after the imaging procedure, and restart XIGDUO XR if renal function is stable.

Surgery and Other Procedures: Withholding of food and fluids during surgical or other procedures may increase the risk for volume depletion, hypotension and renal impairment. XIGDUO XR should be temporarily discontinued while patients have restricted food and fluid intake.

Hypoxic States: Several of the postmarketing cases of metformin-associated lactic acidosis occurred in the setting of acute congestive heart failure (particularly when accompanied by hypoperfusion and hypoxemia). Cardiovascular collapse (shock), acute myocardial infarction, sepsis, and other conditions associated with hypoxemia have been associated with lactic acidosis and may also cause prerenal azotemia. When such events occur, discontinue XIGDUO XR.

Excessive Alcohol Intake: Alcohol potentiates the effect of metformin on lactate metabolism and this may increase the risk of metformin-associated lactic acidosis. Warn patients against excessive alcohol intake while receiving XIGDUO XR.

Hepatic Impairment: Patients with hepatic impairment have developed with cases of metformin-associated lactic acidosis. This may be due to impaired lactate clearance resulting in higher lactate blood levels. Therefore, avoid use of XIGDUO XR in patients with clinical or laboratory evidence of hepatic disease.

5.2 Diabetic Ketoacidosis in Patients with Type 1 Diabetes Mellitus and Other Ketoacidosis

In patients with type 1 diabetes mellitus, dapagliflozin, a component of XIGDUO XR, significantly increases the risk of diabetic ketoacidosis, a life-threatening event, beyond the background rate. In placebo-controlled trials of patients with type 1 diabetes mellitus, the risk of ketoacidosis was markedly increased in patients who received sodium-glucose cotransporter 2 (SGLT2) inhibitors compared to patients who received placebo. XIGDUO XR is not indicated for glycemic control in patients with type 1 diabetes mellitus.

Type 2 diabetes mellitus and pancreatic disorders (e.g., history of pancreatitis or pancreatic surgery) are also risk factors for ketoacidosis. There have been postmarketing reports of fatal events of ketoacidosis in patients with type 2 diabetes mellitus using SGLT2 inhibitors, including dapagliflozin.

Precipitating conditions for diabetic ketoacidosis or other ketoacidosis include under-insulinization due to insulin dose reduction or missed insulin doses, acute febrile illness, reduced caloric intake, ketogenic diet, surgery, volume depletion, and alcohol abuse.

Signs and symptoms are consistent with dehydration and severe metabolic acidosis and include nausea, vomiting, abdominal pain, generalized malaise, and shortness of breath. Blood glucose levels at presentation may be below those typically expected for diabetic ketoacidosis (e.g., less than 250 mg/dL). Ketoacidosis and glucosuria may persist longer than typically expected. Urinary glucose excretion persists for 3 days after discontinuing XIGDUO XR [see Clinical Pharmacology (12.2)]; however, there have been postmarketing reports of ketoacidosis and/or glucosuria lasting greater than 6 days and some up to 2 weeks after discontinuation of SGLT2 inhibitors.

Consider ketone monitoring in patients at risk for ketoacidosis if indicated by the clinical situation. Assess for ketoacidosis regardless of presenting blood glucose levels in patients who present with signs and symptoms consistent with severe metabolic acidosis. If ketoacidosis is suspected, discontinue XIGDUO XR, promptly evaluate, and treat ketoacidosis, if confirmed. Monitor patients for resolution of ketoacidosis before restarting XIGDUO XR.

Withhold XIGDUO XR, if possible, in temporary clinical situations that could predispose patients to ketoacidosis. Resume XIGDUO XR when the patient is clinically stable and has resumed oral intake [see Dosage and Administration (2.6)].

Educate all patients on the signs and symptoms of ketoacidosis and instruct patients to discontinue XIGDUO XR and seek medical attention immediately if signs and symptoms occur.

5.3 Volume Depletion

Dapagliflozin can cause intravascular volume depletion which may sometimes manifest as symptomatic hypotension or acute transient changes in creatinine. There have been post-marketing reports of acute kidney injury, some requiring hospitalization and dialysis, in patients with type 2 diabetes mellitus receiving SGLT2 inhibitors, including dapagliflozin. Patients with impaired renal function (eGFR less than 60 mL/min/1.73 m^2), elderly patients, or patients on loop diuretics may be at increased risk for volume depletion or hypotension. Before initiating XIGDUO XR in patients with one or more of these characteristics, assess volume status and renal function. Monitor for signs and symptoms of hypotension and renal function after initiating therapy.

5.4 Urosepsis and Pyelonephritis

Serious urinary tract infections including urosepsis and pyelonephritis requiring hospitalization have been reported in patients receiving SGLT2 inhibitors, including dapagliflozin. Treatment with SGLT2 inhibitors increases the risk for urinary tract infections. Evaluate patients for signs and symptoms of urinary tract infections and treat promptly, if indicated [see Adverse Reactions (6.2)].

5.5 Hypoglycemia with Concomitant Use with Insulin or Insulin Secretagogues

Insulin and insulin secretagogues (e.g., sulfonylureas) are known to cause hypoglycemia. XIGDUO XR may increase the risk of hypoglycemia when combined with insulin and/or an insulin secretagogue [see Adverse Reactions (6.1)]. The risk of hypoglycemia may be lowered by a reduction in the dose of sulfonylurea (or other concomitantly administered insulin secretagogues) or insulin. Inform patients using these concomitant medications of the risk of hypoglycemia and educate them on the signs and symptoms of hypoglycemia.

5.6 Necrotizing Fasciitis of the Perineum (Fournier’s Gangrene)

Reports of necrotizing fasciitis of the perineum (Fournier’s Gangrene), a rare but serious and life-threatening necrotizing infection requiring urgent surgical intervention, have been identified in postmarketing surveillance in patients with diabetes mellitus receiving SGLT2 inhibitors, including dapagliflozin. Cases have been reported in both females and males. Serious outcomes have included hospitalization, multiple surgeries, and death.

Patients treated with XIGDUO XR presenting with pain or tenderness, erythema, or swelling in the genital or perineal area, along with fever or malaise, should be assessed for necrotizing fasciitis. If suspected, start treatment immediately with broad-spectrum antibiotics and, if necessary, surgical debridement. Discontinue XIGDUO XR, closely monitor blood glucose levels, and provide appropriate alternative therapy for glycemic control.

5.7 Vitamin B12 Concentrations

In controlled clinical trials of metformin of 29-week duration, a decrease to subnormal levels of previously normal serum vitamin B12 levels, without clinical manifestations, was observed in approximately 7% of patients. Such decrease, possibly due to interference with B12 absorption from the B12-intrinsic factor complex, may be associated with anemia but appears to be rapidly reversible with discontinuation of metformin or vitamin B12 supplementation. Certain individuals (those with inadequate vitamin B12 or calcium intake or absorption) appear to be predisposed to developing subnormal vitamin B12 levels. Measure hematologic parameters on an annual basis and vitamin B12 at 2- to 3-year intervals in patients on XIGDUO XR and manage any abnormalities [see Adverse Reactions (6.1)].

5.8 Genital Mycotic Infections

Dapagliflozin increases the risk of genital mycotic infections. Patients with a history of genital mycotic infections were more likely to develop genital mycotic infections [see Adverse Reactions (6.1)]. Monitor and treat appropriately.

6 ADVERSE REACTIONS

The following important adverse reactions are described below and elsewhere in the labeling:

- Lactic Acidosis [see Boxed Warning and Warnings and Precautions (5.1)]
- Diabetic Ketoacidosis in Patients with Type 1 Diabetes Mellitus and Other Ketoacidosis [see Warnings and Precautions (5.2)]
- Volume Depletion [see Warnings and Precautions (5.3)]
- Urosepsis and Pyelonephritis [see Warnings and Precautions (5.4)]
- Hypoglycemia with Concomitant Use with Insulin or Insulin Secretagogues [see Warnings and Precautions (5.5)]
- Necrotizing Fasciitis of the Perineum (Fournier’s Gangrene) [see Warnings and Precautions (5.6)]
- Vitamin B12 Concentrations [see Warnings and Precautions (5.7)]
- Genital Mycotic Infections [see Warnings and Precautions (5.8)]

6.1 Clinical Trials Experience

Because clinical trials are conducted under widely varying conditions, adverse reaction rates observed in the clinical trials of a drug cannot be directly compared to rates in the clinical trials of another drug and may not reflect the rates observed in clinical practice.

Clinical Trials with Metformin HCl Extended-Release in Adults with Type 2 Diabetes Mellitus

In placebo-controlled monotherapy trials of metformin HCl extended-release, diarrhea and nausea/vomiting were reported in >5% of metformin-treated patients and more commonly than in placebo-treated patients (9.6% versus 2.6% for diarrhea and 6.5% versus 1.5% for nausea/vomiting). Diarrhea led to discontinuation of study medication in 0.6% of the patients treated with metformin HCl extended-release.

Clinical Trials with Dapagliflozin in Adults

Dapagliflozin

Dapagliflozin has been evaluated in clinical trials in adult and pediatric patients 10 years of age and older with type 2 diabetes mellitus, in adult patients with heart failure, and in adult patients with chronic kidney disease. The overall safety profile of dapagliflozin was consistent across the studied indications. No new adverse reactions were identified in the DAPA-HF, DELIVER and DAPA-CKD trials.

Pools of Placebo-Controlled Clinical Trials for Glycemic Control in Adults

Pool of 8 Placebo-Controlled Adult Trials for Dapagliflozin and Metformin HCl for Glycemic Control

Data from a prespecified pool of adult patients from 8 short-term, placebo-controlled trials of dapagliflozin coadministered with metformin HCl immediate- or extended-release was used to evaluate safety. This pool included several add-on trials (metformin HCl alone and in combination with a dipeptidyl peptidase-4 [DPP4] inhibitor and metformin HCl, or insulin and metformin HCl, 2 initial combination with metformin HCl trials, and 2 trials of patients with CVD and type 2 diabetes mellitus who received their usual treatment [with metformin HCl as background therapy]). For trials that included background therapy with and without metformin HCl, only patients who received metformin HCl were included in the 8-trial placebo-controlled pool. Across these 8 trials, 983 patients were treated once daily with dapagliflozin 10 mg and metformin HCl, and 1185 were treated with placebo and metformin HCl. These 8 trials provide a mean duration of exposure of 23 weeks. The mean age of the population was 57 years and 2% were older than 75 years. Fifty-four percent (54%) of the population was male; 88% White, 6% Asian, and 3% Black or African American. At baseline, the population had diabetes for an average of 8 years, mean hemoglobin A1c (HbA1c) was 8.4%, and renal function was normal or mildly impaired in 90% of patients and moderately impaired in 10% of patients.

The overall incidence of adverse events for the 8-trial, short-term, placebo-controlled pool in adult patients treated with dapagliflozin 10 mg and metformin HCl was 60.3% compared to 58.2% for the placebo and metformin HCl group. Discontinuation of therapy due to adverse events in patients who received dapagliflozin 10 mg and metformin HCl was 4% compared to 3.3% for the placebo and metformin HCl group. The most commonly reported events leading to discontinuation and reported in at least 3 patients treated with dapagliflozin 10 mg and metformin HCl were renal impairment (0.7%), increased blood creatinine (0.2%), decreased renal creatinine clearance (0.2%), and urinary tract infection (0.2%).

Table 2 shows common adverse reactions in adults associated with the use of dapagliflozin and metformin HCl. These adverse reactions were not present at baseline, occurred more commonly on dapagliflozin and metformin HCl than on placebo, and occurred in at least 2% of patients treated with either dapagliflozin 5 mg or dapagliflozin 10 mg.

Table 2: Adverse Reactions in Placebo-Controlled Trials Reported in ≥2% of Adult Patients Treated with Dapagliflozin and Metformin HCl
Adverse Reaction | % of Patients
Adverse Reaction | Pool of 8 Placebo-Controlled Trials
Adverse Reaction | Placebo and Metformin HCl N=1185 | Dapagliflozin 5 mg and Metformin HCl N=410 | Dapagliflozin 10 mg and Metformin HCl N=983
Female genital mycotic infections [Genital mycotic infections include the following adverse reactions, listed in order of frequency reported for females: vulvovaginal mycotic infection, vaginal infection, genital infection, vulvovaginitis, fungal genital infection, vulvovaginal candidiasis, vulval abscess, genital candidiasis, and vaginitis bacterial. (N for females: Placebo and metformin HCl=534, dapagliflozin 5 mg and metformin HCl=223, dapagliflozin 10 mg and metformin HCl=430).] | 1.5 | 9.4 | 9.3
Nasopharyngitis | 5.9 | 6.3 | 5.2
Urinary tract infections [Urinary tract infections include the following adverse reactions, listed in order of frequency reported: urinary tract infection, cystitis, pyelonephritis, urethritis, and prostatitis.] | 3.6 | 6.1 | 5.5
Diarrhea | 5.6 | 5.9 | 4.2
Headache | 2.8 | 5.4 | 3.3
Male genital mycotic infections [Genital mycotic infections include the following adverse reactions, listed in order of frequency reported for males: balanitis, fungal genital infection, balanitis candida, genital candidiasis, genital infection, posthitis, and balanoposthitis. (N for males: Placebo and metformin HCl=651, dapagliflozin 5 mg and metformin HCl=187, dapagliflozin 10 mg and metformin HCl=553).] | 0 | 4.3 | 3.6
Influenza | 2.4 | 4.1 | 2.6
Nausea | 2.0 | 3.9 | 2.6
Back pain | 3.2 | 3.4 | 2.5
Dizziness | 2.2 | 3.2 | 1.8
Cough | 1.9 | 3.2 | 1.4
Constipation | 1.6 | 2.9 | 1.9
Dyslipidemia | 1.4 | 2.7 | 1.5
Pharyngitis | 1.1 | 2.7 | 1.5
Increased urination [Increased urination includes the following adverse reactions, listed in order of frequency reported: pollakiuria, polyuria, and urine output increased.] | 1.4 | 2.4 | 2.6
Discomfort with urination | 1.1 | 2.2 | 1.6

Pool of 12 Placebo-Controlled Adult Trials for Dapagliflozin 5 and 10 mg for Glycemic Control

The data in Table 3 are derived from 12 glycemic control placebo-controlled trials in adults ranging from 12 to 24 weeks. In 4 trials dapagliflozin was used as monotherapy, and in 8 trials dapagliflozin was used as add-on to background antidiabetic therapy or as combination therapy with metformin HCl [see Clinical Studies (14.1)].

These data reflect exposure of 2338 adult patients to dapagliflozin with a mean exposure duration of 21 weeks. Patients received placebo (N=1393), dapagliflozin 5 mg (N=1145), or dapagliflozin 10 mg (N=1193) once daily. The mean age of the population was 55 years and 2% were older than 75 years of age. Fifty percent (50%) of the population were male; 81% were White, 14% were Asian, and 3% were Black or African American. At baseline, the population had diabetes for an average of 6 years, had a mean HbA1c of 8.3%, and 21% had established microvascular complications of diabetes. Baseline renal function was normal or mildly impaired in 92% of patients and moderately impaired in 8% of patients (mean eGFR 86 mL/min/1.73 m^2).

Table 3 shows common adverse reactions in adults associated with the use of dapagliflozin. These adverse reactions were not present at baseline, occurred more commonly on dapagliflozin than on placebo, and occurred in at least 2% of patients treated with either dapagliflozin 5 mg or dapagliflozin 10 mg.

Table 3: Adverse Reactions in Placebo-Controlled Trials of Glycemic Control Reported in ≥2% of Adults Treated with Dapagliflozin
Adverse Reaction | % of Patients
Adverse Reaction | Pool of 12 Placebo-Controlled Trials
Adverse Reaction | Placebo N=1393 | Dapagliflozin 5 mg N=1145 | Dapagliflozin 10 mg N=1193
Female genital mycotic infections [Genital mycotic infections include the following adverse reactions, listed in order of frequency reported for females: vulvovaginal mycotic infection, vaginal infection, vulvovaginal candidiasis, vulvovaginitis, genital infection, genital candidiasis, fungal genital infection, vulvitis, genitourinary tract infection, vulval abscess, and vaginitis bacterial. (N for females: Placebo=677, dapagliflozin 5 mg=581, dapagliflozin 10 mg=598).] | 1.5 | 8.4 | 6.9
Nasopharyngitis | 6.2 | 6.6 | 6.3
Urinary tract infections [Urinary tract infections include the following adverse reactions, listed in order of frequency reported: urinary tract infection, cystitis, Escherichia urinary tract infection, genitourinary tract infection, pyelonephritis, trigonitis, urethritis, kidney infection, and prostatitis.] | 3.7 | 5.7 | 4.3
Back pain | 3.2 | 3.1 | 4.2
Increased urination [Increased urination includes the following adverse reactions, listed in order of frequency reported: pollakiuria, polyuria, and urine output increased.] | 1.7 | 2.9 | 3.8
Male genital mycotic infections [Genital mycotic infections include the following adverse reactions, listed in order of frequency reported for males: balanitis, fungal genital infection, balanitis candida, genital candidiasis, genital infection male, penile infection, balanoposthitis, balanoposthitis infective, genital infection, and posthitis. (N for males: Placebo=716, dapagliflozin 5 mg=564, dapagliflozin 10 mg=595).] | 0.3 | 2.8 | 2.7
Nausea | 2.4 | 2.8 | 2.5
Influenza | 2.3 | 2.7 | 2.3
Dyslipidemia | 1.5 | 2.1 | 2.5
Constipation | 1.5 | 2.2 | 1.9
Discomfort with urination | 0.7 | 1.6 | 2.1
Pain in extremity | 1.4 | 2.0 | 1.7

Pool of 13 Placebo-Controlled Adult Trials for Dapagliflozin 10 mg for Glycemic Control

Dapagliflozin 10 mg was also evaluated in a larger glycemic control placebo-controlled trial pool in adult patients. This pool combined 13 placebo-controlled trials, including 3 monotherapy trials, 9 add-on to background antidiabetic therapy trials, and an initial combination with metformin HCl trial. Across these 13 trials, 2360 patients were treated once daily with dapagliflozin 10 mg for a mean duration of exposure of 22 weeks. The mean age of the population was 59 years and 4% were older than 75 years. Fifty-eight percent (58%) of the population were male; 84% were White, 9% were Asian, and 3% were Black or African American. At baseline, the population had diabetes for an average of 9 years, had a mean HbA1c of 8.2%, and 30% had established microvascular disease. Baseline renal function was normal or mildly impaired in 88% of patients and moderately impaired in 11% of patients (mean eGFR 82 mL/min/1.73 m^2).

Other Adverse Reactions with Dapagliflozin in Adults with Type 2 Diabetes Mellitus

Volume Depletion

Dapagliflozin causes an osmotic diuresis, which may lead to a reduction in intravascular volume. Adverse reactions related to volume depletion (including reports of dehydration, hypovolemia, orthostatic hypotension, or hypotension) for the 12-trial and 13-trial, short-term, placebo-controlled pools and for the DECLARE trial are shown in Table 4 [see Warnings and Precautions (5.3)].

Table 4: Adverse Reactions Related to Volume Depletion [Volume depletion includes reports of dehydration, hypovolemia, orthostatic hypotension, or hypotension.] in Adult Clinical Trials with Dapagliflozin
 | Pool of 12 Placebo-Controlled Trials |  |  | Pool of 13 Placebo-Controlled Trials |  | DECLARE Trial
 | Placebo | Dapagliflozin; 5 mg | Dapagliflozin; 10 mg | Placebo | Dapagliflozin; 10 mg | Placebo | Dapagliflozin; 10 mg
Overall population; N (%) | N=1393; 5; (0.4%) | N=1145; 7; (0.6%) | N=1193; 9; (0.8%) | N=2295; 17; (0.7%) | N=2360; 27; (1.1%) | N=8569; 207; (2.4%) | N=8574; 213; (2.5%)
Patient Subgroup n (%)
Patients on loop diuretics | n=55; 1; (1.8%) | n=40; 0 | n=31; 3; (9.7%) | n=267; 4; (1.5%) | n=236; 6; (2.5%) | n=934; 57; (6.1%) | n=866; 57; (6.6%)
Patients with moderate renal impairment with eGFR ≥30 and <60 mL/min/1.73 m^2 | n=107; 2; (1.9%) | n=107; 1; (0.9%) | n=89; 1; (1.1%) | n=268; 4; (1.5%) | n=265; 5; (1.9%) | n=658; 30; (4.6%) | n=604; 35; (5.8%)
Patients ≥65 years of age | n=276; 1; (0.4%) | n=216; 1; (0.5%) | n=204; 3; (1.5%) | n=711; 6; (0.8%) | n=665; 11; (1.7%) | n=3950; 121; (3.1%) | n=3948; 117; (3.0%)

Hypoglycemia

The frequency of hypoglycemia in adult patients by trial [see Clinical Studies (14.1)] is shown in Table 5. Hypoglycemia was more frequent when dapagliflozin was added to sulfonylurea or insulin [see Warnings and Precautions (5.5)].

Table 5: Incidence of Severe Hypoglycemia [Severe episodes of hypoglycemia were defined as episodes of severe impairment in consciousness or behavior, requiring external (third party) assistance, and with prompt recovery after intervention regardless of glucose level.] and Hypoglycemia with Glucose < 54 mg/dL [Episodes of hypoglycemia with glucose < 54 mg/dL (3 mmol/L) were defined as reported episodes of hypoglycemia meeting the glucose criteria that did not also qualify as a severe episode.] in Controlled Glycemic Control Clinical Trials in Adults
 | Placebo | Dapagliflozin; 5 mg | Dapagliflozin; 10 mg
Add-on to Metformin HCl (24 weeks) | N=137 | N=137 | N=135
Severe [n (%)] | 0 | 0 | 0
Glucose < 54 mg/dL [n (%)] | 0 | 0 | 0
Add-on to DPP4 inhibitor (with or without Metformin HCl) (24 weeks) | N=226 | – | N=225
Severe [n (%)] | 0 | – | 1 (0.4)
Glucose < 54 mg/dL [n (%)] | 1 (0.4) | – | 1 (0.4)
Add-on to Insulin with or without other OADs [OAD = oral antidiabetic therapy.] (24 weeks) | N=197 | N=212 | N=196
Severe [n (%)] | 1 (0.5) | 2 (0.9) | 2 (1.0)
Glucose < 54 mg/dL [n (%)] | 43 (21.8) | 55 (25.9) | 45 (23.0)

In the DECLARE trial [see Clinical Studies (14.3)], severe events of hypoglycemia were reported in 58 (0.7%) out of 8574 adult patients treated with dapagliflozin 10 mg and 83 (1.0%) out of 8569 adult patients treated with placebo.

Genital Mycotic Infections

In the glycemic control trials in adults, genital mycotic infections were more frequent with dapagliflozin treatment. Genital mycotic infections were reported in 0.9% of patients on placebo, 5.7% on dapagliflozin 5 mg, and 4.8% on dapagliflozin 10 mg, in the 12-trial placebo-controlled pool. Discontinuation from trial due to genital infection occurred in 0% of placebo-treated patients and 0.2% of patients treated with dapagliflozin 10 mg. Infections were more frequently reported in females than in males (see Table 3). The most frequently reported genital mycotic infections were vulvovaginal mycotic infections in females and balanitis in males. Patients with a history of genital mycotic infections were more likely to have a genital mycotic infection during the trial than those with no prior history (10.0%, 23.1%, and 25.0% versus 0.8%, 5.9%, and 5.0% on placebo, dapagliflozin 5 mg, and dapagliflozin 10 mg, respectively). In the DECLARE trial [see Clinical Studies (14.3)], serious genital mycotic infections were reported in <0.1% of patients treated with dapagliflozin 10 mg and <0.1% of patients treated with placebo. Genital mycotic infections that caused trial drug discontinuation were reported in 0.9% of patients treated with dapagliflozin 10 mg and <0.1% of patients treated with placebo.

Hypersensitivity Reactions

Hypersensitivity reactions (e.g., angioedema, urticaria, hypersensitivity) were reported with dapagliflozin treatment. In glycemic control trials in adults, serious anaphylactic reactions and severe cutaneous adverse reactions and angioedema were reported in 0.2% of comparator-treated patients and 0.3% of dapagliflozin-treated patients. If hypersensitivity reactions occur, discontinue use of dapagliflozin; treat per standard of care and monitor until signs and symptoms resolve.

Ketoacidosis

In the DECLARE trial [see Clinical Studies (14.3)], events of diabetic ketoacidosis (DKA) were reported in 27 out of 8574 adult patients in the dapagliflozin-treated group and in 12 out of 8569 adult patients in the placebo group. The events were evenly distributed over the trial period.

Laboratory Tests in Adults with Type 2 Diabetes Mellitus treated with Dapagliflozin or Metformin HCl

Dapagliflozin

Increases in Serum Creatinine and Decreases in eGFR

Initiation of SGLT2 inhibitors, including dapagliflozin, causes a small increase in serum creatinine and decrease in eGFR. These changes in serum creatinine and eGFR generally occur within two weeks of starting therapy and then stabilize regardless of baseline kidney function. Changes that do not fit this pattern should prompt further evaluation to exclude the possibility of acute kidney injury [see Warnings and Precautions (5.3)]. In two trials that included adult patients with type 2 diabetes mellitus with moderate renal impairment, the acute effect on eGFR reversed after treatment discontinuation, suggesting acute hemodynamic changes may play a role in the renal function changes observed with dapagliflozin.

Increase in Hematocrit

In the pool of 13 placebo-controlled trials of glycemic control, increases from baseline in mean hematocrit values were observed in dapagliflozin-treated adult patients starting at Week 1 and continuing up to Week 16, when the maximum mean difference from baseline was observed. At Week 24, the mean changes from baseline in hematocrit were -0.33% in the placebo group and 2.30% in the dapagliflozin 10 mg group. By Week 24, hematocrit values >55% were reported in 0.4% of placebo-treated patients and 1.3% of dapagliflozin 10 mg‑treated patients.

Increase in Low-Density Lipoprotein Cholesterol

In the pool of 13 placebo-controlled trials of glycemic control, changes from baseline in mean lipid values were reported in dapagliflozin-treated adult patients compared to placebo-treated patients. Mean percent changes from baseline at Week 24 were 0.0% versus 2.5% for total cholesterol, and -1.0% versus 2.9% for LDL cholesterol in the placebo and dapagliflozin 10 mg groups, respectively. In the DECLARE trial [see Clinical Studies (14.3)], mean changes from baseline after 4 years were 0.4 mg/dL versus ‑4.1 mg/dL for total cholesterol, and ‑2.5 mg/dL versus ‑4.4 mg/dL for LDL cholesterol, in dapagliflozin 10 mg‑treated and the placebo groups, respectively.

Decrease in Serum Bicarbonate

In a trial of concomitant therapy of dapagliflozin 10 mg with exenatide extended release (on a background of metformin HCl) in adults, four patients (1.7%) on concomitant therapy had a serum bicarbonate value of less than or equal to 13 mEq/L compared to one each (0.4%) in the dapagliflozin and exenatide extended release treatment groups [see Warning and Precautions (5.2)].

Metformin HCl

Vitamin B12 Concentrations

In metformin clinical trials of 29‑week duration, a decrease to subnormal levels of previously normal serum vitamin B12 levels was observed in approximately 7% of patients.

Clinical Trials in Pediatric Patients Aged 10 to 17 Years with Type 2 Diabetes Mellitus

Dapagliflozin

The dapagliflozin safety profile observed in the 26-week placebo-controlled clinical trial with a 26-week extension in 157 pediatric patients aged 10 years and older with type 2 diabetes mellitus was similar to that observed in adults [see Clinical Studies (14.2)].

Metformin HCl

In clinical trials with metformin HCl immediate-release tablets in pediatric patients with type 2 diabetes mellitus, the profile of adverse reactions was similar to that observed in adults.

6.2 Postmarketing Experience

Additional adverse reactions have been identified during post‑approval use of XIGDUO XR, dapagliflozin or metformin HCl. Because these reactions are reported voluntarily from a population of uncertain size, it is generally not possible to reliably estimate their frequency or establish a causal relationship to drug exposure.

Dapagliflozin

Infections: Necrotizing fasciitis of the perineum (Fournier’s Gangrene), urosepsis and pyelonephritis

Metabolism and Nutrition Disorders: Ketoacidosis

Renal and Urinary Disorders: Acute kidney injury

Skin and Subcutaneous Tissue Disorders: Rash

Metformin HCl

Hepatobiliary Disorders: Cholestatic, hepatocellular, and mixed hepatocellular liver injury

7 DRUG INTERACTIONS

Table 6: Clinically Relevant Interactions with XIGDUO XR
Carbonic Anhydrase Inhibitors
Clinical Impact | Topiramate or other carbonic anhydrase inhibitors (e.g., zonisamide, acetazolamide or dichlorphenamide) frequently causes a decrease in serum bicarbonate and induce non-anion gap, hyperchloremic metabolic acidosis. Concomitant use of these drugs with XIGDUO XR may increase the risk for lactic acidosis.
Intervention | Consider more frequent monitoring of these patients.
Drugs that Reduce Metformin Clearance
Clinical Impact | Concomitant use of drugs that interfere with common renal tubular transport systems involved in the renal elimination of metformin (e.g., organic cationic transporter-2 [OCT2]/multidrug and toxin extrusion [MATE] inhibitors, such as ranolazine, vandetanib, dolutegravir, and cimetidine) could increase systemic exposure to metformin and may increase the risk for lactic acidosis [see Clinical Pharmacology (12.3)].
Intervention | Consider the benefits and risks of concomitant use.
Alcohol
Clinical Impact | Alcohol is known to potentiate the effect of metformin on lactate metabolism.
Intervention | Warn patients against excessive alcohol intake while receiving XIGDUO XR.
Insulin or Insulin Secretagogues
Clinical Impact | The risk of hypoglycemia may be increased when XIGDUO XR is used concomitantly with insulin or insulin secretagogues (e.g., sulfonylurea) [see Warnings and Precautions (5.5)].
Intervention | Concomitant use may require lower doses of insulin or the insulin secretagogue to reduce the risk of hypoglycemia.
Drugs Affecting Glycemic Control
Clinical Impact | Certain drugs tend to produce hyperglycemia and may lead to loss of glycemic control. These medications include thiazides and other diuretics, corticosteroids, phenothiazines, thyroid products, estrogens, oral contraceptives, phenytoin, nicotinic acid, sympathomimetics, calcium channel blocking drugs, and isoniazid.
Intervention | When such drugs are administered to a patient receiving XIGDUO XR, observe the patient closely for loss of blood glucose control. When such drugs are withdrawn from a patient receiving XIGDUO XR, observe the patient closely for hypoglycemia.
Lithium
Clinical Impact | Concomitant use of an SGLT2 inhibitor with lithium may decrease serum lithium concentrations.
Intervention | Monitor serum lithium concentration more frequently during XIGDUO XR initiation and dosage changes.
Positive Urine Glucose Test
Clinical Impact | SGLT2 inhibitors increase urinary glucose excretion and will lead to positive urine glucose tests.
Intervention | Monitoring glycemic control with urine glucose tests is not recommended in patients taking SGLT2 inhibitors. Use alternative methods to monitor glycemic control.
Interference with 1,5-anhydroglucitol (1,5-AG) Assay
Clinical Impact | Measurements of 1,5-AG are unreliable in assessing glycemic control in patients taking SGLT2 inhibitors.
Intervention | Monitoring glycemic control with 1,5-AG assay is not recommended. Use alternative methods to monitor glycemic control.

8 USE IN SPECIFIC POPULATIONS

8.1 Pregnancy

Risk Summary

Based on animal data showing adverse renal effects, XIGDUO XR is not recommended during the second and third trimesters of pregnancy.

Limited data with XIGDUO XR or dapagliflozin in pregnant women are not sufficient to determine drug‑associated risk for major birth defects or miscarriage. Published studies with metformin use during pregnancy have not reported a clear association with metformin and major birth defect or miscarriage risk (see Data). There are risks to the mother and fetus associated with poorly controlled diabetes in pregnancy (see Clinical Considerations).

In animal studies, adverse renal pelvic and tubule dilatations, that were not fully reversible, were observed in rats when dapagliflozin was administered during a period of renal development corresponding to the late second and third trimesters of human pregnancy, at all doses tested; the lowest of which provided an exposure 15-times the 10 mg clinical dose (see Data).

The estimated background risk of major birth defects is 6 to 10% in women with pre-gestational diabetes with a HbA1c greater than 7% and has been reported to be as high as 20 to 25% in women with HbA1c greater than 10%. The estimated background risk of miscarriage for the indicated population is unknown. In the U.S. general population, the estimated background risk of major birth defects and miscarriage in clinically recognized pregnancies is 2 to 4% and 15 to 20%, respectively.

Clinical Considerations

Disease-associated maternal and/or embryofetal risk

Poorly controlled diabetes in pregnancy increases the maternal risk for diabetic ketoacidosis, preeclampsia, spontaneous abortions, preterm delivery and delivery complications. Poorly controlled diabetes increases the fetal risk for major birth defects, stillbirth, and macrosomia related morbidity.

Data

Human Data

Published data from post-marketing studies have not reported a clear association with metformin and major birth defects, miscarriage, or adverse maternal or fetal outcomes when metformin was used during pregnancy. However, these studies cannot definitely establish the absence of any metformin-associated risk because of methodological limitations, including small sample size and inconsistent comparator groups.

Animal Data

Dapagliflozin

Dapagliflozin dosed directly to juvenile rats from postnatal day (PND) 21 until PND 90 at doses of 1, 15, or 75 mg/kg/day, increased kidney weights and increased the incidence of renal pelvic and tubular dilatations at all dose levels. Exposure at the lowest dose tested was 15-times the 10 mg clinical dose (based on AUC). The renal pelvic and tubular dilatations observed in juvenile animals did not fully reverse within a 1-month recovery period.

In a prenatal and postnatal development study, dapagliflozin was administered to maternal rats from gestation day 6 through lactation day 21 at doses of 1, 15, or 75 mg/kg/day, and pups were indirectly exposed in utero and throughout lactation. Increased incidence or severity of renal pelvic dilatation was observed in 21-day-old pups offspring of treated dams at 75 mg/kg/day (maternal and pup dapagliflozin exposures were 1415-times and 137-times, respectively, the human values at the 10 mg clinical dose, based on AUC). Dose-related reductions in pup body weights were observed at greater or equal to 29-times the 10 mg clinical dose (based on AUC). No adverse effects on developmental endpoints were noted at 1 mg/kg/day (19-times the 10 mg clinical dose, based on AUC). These outcomes occurred with drug exposure during periods of renal development in rats that corresponds to the late second and third trimester of human development.

In embryofetal development studies in rats and rabbits, dapagliflozin was administered throughout organogenesis, corresponding to the first trimester of human pregnancy. In rats, dapagliflozin was neither embryolethal nor teratogenic at doses up to 75 mg/kg/day (1441-times the 10 mg clinical dose, based on AUC). Dose‑related effects on the rat fetus (structural abnormalities and reduced body weight) occurred only at higher dosages, equal to or greater than 150 mg/kg (more than 2344-times the 10 mg clinical dose, based on AUC), which were associated with maternal toxicity. No developmental toxicities were observed in rabbits at doses up to 180 mg/kg/day (1191-times the 10 mg clinical dose, based on AUC).

Metformin HCl

Metformin HCl did not cause adverse developmental effects when administered to pregnant Sprague Dawley rats and rabbits up to 600 mg/kg/day during the period of organogenesis. This represents an exposure of about 2- and 6-times a 2,000 mg clinical dose based on body surface area (mg/m^2) for rats and rabbits, respectively. Determination of fetal concentrations demonstrated a partial placental barrier to metformin.

8.2 Lactation

Risk Summary

There is no information regarding the presence of XIGDUO XR or dapagliflozin in human milk, the effects on the breastfed infant, or the effects on milk production.

Limited published studies report that metformin is present in human milk (see Data). However, there is insufficient information on the effects of metformin on the breastfed infant and no available information on the effects of metformin on milk production. Dapagliflozin is present in the milk of lactating rats (see Data). However, due to species specific differences in lactation physiology, the clinical relevance of these data is not clear. Since human kidney maturation occurs in utero and during the first 2 years of life when lactational exposure may occur, there may be risk to the developing human kidney.

Because of the potential for serious adverse reactions in breastfed infants, advise women that use of XIGDUO XR is not recommended while breastfeeding.

Data

Dapagliflozin

Dapagliflozin was present in rat milk at a milk/plasma ratio of 0.49, indicating that dapagliflozin and its metabolites are transferred into milk at a concentration that is approximately 50% of that in maternal plasma. Juvenile rats directly exposed to dapagliflozin showed risk to the developing kidney (renal pelvic and tubular dilatations) during maturation.

Metformin HCl

Published clinical lactation studies report that metformin is present in human milk which resulted in infant doses approximately 0.11% to 1% of the maternal weight-adjusted dosage and a milk/plasma ratio ranging between 0.13 and 1. However, the studies were not designed to definitely establish the risk of use of metformin during lactation because of small sample size and limited adverse event data collected in infants.

8.3 Females and Males of Reproductive Potential

Discuss the potential for unintended pregnancy with premenopausal women as therapy with metformin may result in ovulation in some anovulatory women.

8.4 Pediatric Use

The safety and effectiveness of XIGDUO XR as an adjunct to diet and exercise to improve glycemic control in type 2 diabetes mellitus have been established in pediatric patients aged 10 years and older.

Use of XIGDUO XR for this indication is supported by a 26‑week placebo-controlled trial of dapagliflozin with a 26‑week extension in 157 pediatric patients aged 10 to 17 years with type 2 diabetes mellitus, pediatric pharmacokinetic data, and trials in adults with type 2 diabetes mellitus [see Clinical Pharmacology (12.3) and Clinical Studies (14.1, 14.2)]. The safety profile observed in the placebo-controlled trial of dapagliflozin in pediatric patients with type 2 diabetes mellitus was similar to that observed in adults [see Adverse Reactions (6.1)].

The use of XIGDUO XR for this indication is also supported by evidence from adequate and well-controlled trials of metformin HCl immediate-release tablets in adults with additional data from a controlled clinical trial using metformin HCl immediate-release tablets in pediatric patients 10 to 16 years old with type 2 diabetes mellitus, and pharmacokinetic data with metformin HCl extended-release tablets in adults [see Clinical Pharmacology (12.3) and Clinical Studies (14.1, 14.2)]. In the clinical trial with pediatric patients receiving metformin HCl immediate-release tablets, adverse reactions with metformin HCl immediate-release tablets were similar to those described in adults [see Adverse Reactions (6.1)].

The safety and effectiveness of XIGDUO XR for glycemic control in patients with type 2 diabetes mellitus have not been established in pediatric patients less than 10 years of age.

The safety and effectiveness of XIGDUO XR have not been established in pediatric patients to reduce the risk of [see Indications and Usage (1)]:

- sustained eGFR decline, end stage kidney disease, cardiovascular death, and hospitalization for heart failure in patients with chronic kidney disease at risk of progression.
- cardiovascular death, hospitalization for heart failure, and urgent heart failure visit in patients with heart failure.
- hospitalization for heart failure in patients with type 2 diabetes mellitus and either established cardiovascular disease (CVD) or multiple cardiovascular (CV) risk factors.

8.5 Geriatric Use

XIGDUO XR

No XIGDUO XR dosage change is recommended based on age. More frequent assessment of renal function is recommended in elderly patients.

Dapagliflozin

A total of 1424 (24%) of the 5936 dapagliflozin-treated patients were 65 years and older and 207 (3.5%) patients were 75 years and older in a pool of 21 double-blind, controlled, clinical trials assessing the efficacy of dapagliflozin in improving glycemic control. After controlling for level of renal function (eGFR), efficacy was similar for patients under age 65 years and those 65 years and older. In patients ≥65 years of age, a higher proportion of patients treated with dapagliflozin for glycemic control had adverse reactions of hypotension [see Warnings and Precautions (5.3) and Adverse Reactions (6.1)].

In the DAPA-HF, DELIVER and DAPA-CKD trials, safety and efficacy were similar for patients aged 65 years and younger and those older than 65 in both the overall population and in the patients with type 2 diabetes mellitus. In the DAPA HF trial, 2714 (57%) out of 4744 patients with heart failure with reduced ejection fraction (HFrEF) were older than 65 years. Out of 2139 patients with HFrEF and type 2 diabetes mellitus, 1211 (57%) were older than 65 years. In the DELIVER trial, 4759 (76%) out of 6263 patients with heart failure (LVEF >40%) were older than 65 years. Out of 2806 patients with LVEF >40% and type 2 diabetes mellitus, 2072 (74%) were older than 65 years. In the DAPA-CKD trial, 1818 (42%) out of 4304 patients with chronic kidney disease were older than 65 years. Out of 2906 patients with chronic kidney disease and type 2 diabetes mellitus, 1399 (48%) were older than 65 years.

Metformin HCl

Controlled clinical trials of metformin did not include sufficient numbers of elderly patients to determine whether they respond differently than younger patients. In general, dosage selection for an elderly patient should be cautious, usually starting at the low end of the dosing range, reflecting the greater frequency of decreased hepatic, renal, or cardiac function, and of concomitant disease or other drug therapy and the higher risk of lactic acidosis. Assess renal function more frequently in elderly patients [see Warnings and Precautions (5.1)].

8.6 Renal Impairment

Initiation of XIGDUO XR is not recommended in patients with an eGFR below 45 mL/min/1.73 m^2 and is contraindicated in patients with severe renal impairment (eGFR less than 30 mL/min/1.73 m^2) or end‑stage renal disease [see Dosage and Administration (2.4), Contraindications (4) and Warnings and Precautions (5.1, 5.3)].

Dapagliflozin

Dapagliflozin 10 mg was evaluated in 4304 adult patients with chronic kidney disease (eGFR 25 to 75 mL/min/1.73 m^2) in the DAPA-CKD trial. Dapagliflozin 10 mg was also evaluated in 1926 adult patients with an eGFR of 30 to 60 mL/min/1.73 m2 in the DAPA-HF trial. The safety profile of dapagliflozin across eGFR subgroups was consistent with the known safety profile [see Adverse Reactions (6.1) and Clinical Studies (14.4 and 14.5)].

Dapagliflozin 10 mg was evaluated in two glycemic control trials that included adult patients with moderate renal impairment (an eGFR of 45 to less than 60 mL/min/1.73 m^2, and an eGFR of 30 to less than 60 mL/min/1.73 m^2) [see Clinical Studies (14.1)]. Patients with diabetes and renal impairment using dapagliflozin 10 mg are more likely to experience hypotension and may be at higher risk for acute kidney injury secondary to volume depletion. In the trial of adult patients with an eGFR 30 to less than 60 mL/min/1.73 m^2, 13 patients receiving dapagliflozin experienced bone fractures compared to none receiving placebo. Use of dapagliflozin 10 mg for glycemic control in patients without established CV disease or CV risk factors is not recommended when eGFR is less than 45 mL/min/1.73 m^2 [see Dosage and Administration (2.4)].

Metformin HCl

Metformin is substantially excreted by the kidney, and the risk of metformin accumulation and lactic acidosis increases with the degree of renal impairment. XIGDUO XR is contraindicated in severe renal impairment, patients with an estimated glomerular filtration rate (eGFR) below 30 mL/min/1.73 m^2 [see Dosage and Administration (2.4), Contraindications (4), Warnings and Precautions (5.1), and Clinical Pharmacology (12.3)].

8.7 Hepatic Impairment

Use of metformin in patients with hepatic impairment has been associated with some cases of lactic acidosis. XIGDUO XR is not recommended in patients with hepatic impairment [see Warnings and Precautions (5.1)].

10 OVERDOSAGE

Dapagliflozin

In the event of an overdose, consider contacting the Poison Help line (1-800-222-1222) or a medical toxicologist for additional overdosage management recommendations. The removal of dapagliflozin by hemodialysis has not been studied.

Metformin HCl

Overdose of metformin HCl has occurred, including ingestion of amounts >50 grams. Lactic acidosis has been reported in approximately 32% of metformin overdose cases [see Warnings and Precautions (5.1)]. Metformin is dialyzable with a clearance of up to 170 mL/min under good hemodynamic conditions. Therefore, hemodialysis may be useful for removal of accumulated drug from patients in whom metformin overdosage is suspected.

11 DESCRIPTION

XIGDUO XR tablets contain: dapagliflozin, a SGLT2 inhibitor, and metformin HCl, a biguanide.

Dapagliflozin

Dapagliflozin is described chemically as D-glucitol, 1,5-anhydro-1-C-[4-chloro-3-[(4-ethoxyphenyl)methyl]phenyl]-, (1S)-, compounded with (2S)-1,2-propanediol, hydrate (1:1:1). The empirical formula is C21H25ClO6•C3H8O2•H2O and the formula weight is 502.98. The structural formula is:

Metformin HCl

Metformin HCl (N,N-dimethylimidodicarbonimidic diamide HCl) is a white to off-white crystalline compound with a molecular formula of C4H11N5•HCl and a molecular weight of 165.63. Metformin HCl is freely soluble in water, slightly soluble in alcohol, and is practically insoluble in acetone, ether, and chloroform. The pKa of metformin is 12.4. The pH of a 1% aqueous solution of metformin HCl is 6.68. The structural formula is:

XIGDUO XR

XIGDUO XR is available for oral administration as tablets containing the equivalent of 2.5 mg dapagliflozin as dapagliflozin propanediol and 1,000 mg metformin HCl which is equivalent to 779.86 mg metformin base (XIGDUO XR 2.5 mg/1,000 mg), 5 mg dapagliflozin as dapagliflozin propanediol and 500 mg metformin HCl which is equivalent to 389.9 mg metformin base (XIGDUO XR 5 mg/500 mg), the equivalent of 5 mg dapagliflozin as dapagliflozin propanediol and 1,000 mg metformin HCl which is equivalent to 779.86 mg metformin base (XIGDUO XR 5 mg/1,000 mg), the equivalent of 10 mg dapagliflozin as dapagliflozin propanediol and 500 mg metformin HCl which is equivalent to 389.9 mg metformin base (XIGDUO XR 10 mg/500 mg), or the equivalent of 10 mg dapagliflozin as dapagliflozin propanediol and 1,000 mg metformin HCl which is equivalent to 779.86 mg metformin base (XIGDUO XR 10 mg/1,000 mg).

Each film-coated tablet of XIGDUO XR contains the following inactive ingredients: anhydrous lactose, carboxymethylcellulose sodium, crospovidone, hypromellose, magnesium stearate, microcrystalline cellulose, and silicon dioxide.

The film coatings contain the following inactive ingredients: polyethylene glycol, polyvinyl alcohol, talc, and titanium dioxide. Additionally, the film coating for the XIGDUO XR 5 mg/500 mg tablets contains FD&C Yellow No. 6/Sunset Yellow FCF aluminum lake. The film coating for the XIGDUO XR 2.5 mg/1,000 mg, 5 mg/1,000 mg, 10 mg/500 mg, and 10 mg/1,000 mg tablets contains iron oxides.

12 CLINICAL PHARMACOLOGY

12.1 Mechanism of Action

Dapagliflozin

Sodium-glucose cotransporter 2 (SGLT2), expressed in the proximal renal tubules, is responsible for the majority of the reabsorption of filtered glucose from the tubular lumen. Dapagliflozin is an inhibitor of SGLT2. By inhibiting SGLT2, dapagliflozin reduces reabsorption of filtered glucose, and thereby promotes urinary glucose excretion.

Dapagliflozin also reduces sodium reabsorption and increases the delivery of sodium to the distal tubule. This may influence several physiological functions including, but not restricted to, lowering both pre- and afterload of the heart and downregulation of sympathetic activity, and decreased intraglomerular pressure which is believed to be mediated by increased tubuloglomerular feedback.

Metformin HCl

Metformin is an antihyperglycemic agent which improves glucose tolerance in patients with type 2 diabetes mellitus, lowering both basal and postprandial plasma glucose. Metformin decreases hepatic glucose production, decreases intestinal absorption of glucose, and improves insulin sensitivity by increasing peripheral glucose uptake and utilization. With metformin therapy, insulin secretion remains unchanged while fasting insulin levels and day-long plasma insulin response may decrease.

12.2 Pharmacodynamics

General

Dapagliflozin

Increases in the amount of glucose excreted in the urine were observed in healthy subjects and in patients with type 2 diabetes mellitus following the administration of dapagliflozin (see Figure 1). Dapagliflozin doses of 5 or 10 mg per day in patients with type 2 diabetes mellitus for 12 weeks resulted in excretion of approximately 70 grams of glucose in the urine per day. A near maximum glucose excretion was observed at the dapagliflozin daily dosage of 20 mg. This urinary glucose excretion with dapagliflozin also results in increases in urinary volume [see Adverse Reactions (6.1)]. After discontinuation of dapagliflozin, on average, the elevation in urinary glucose excretion approaches baseline by about 3 days for the 10 mg dosage.

Figure 1: Scatter Plot and Fitted Line of Change from Baseline in 24-Hour Urinary Glucose Amount versus Dapagliflozin Dose in Healthy Subjects and Subjects with Type 2 Diabetes Mellitus (T2DM) (Semi-Log Plot)

Cardiac Electrophysiology

Dapagliflozin was not associated with clinically meaningful prolongation of QTc interval at daily doses up to 150 mg (15-times the recommended maximum dose) in a study of healthy subjects. In addition, no clinically meaningful effect on QTc interval was observed following single doses of up to 500 mg (50-times the recommended maximum dose) of dapagliflozin in healthy subjects.

12.3 Pharmacokinetics

XIGDUO XR

The administration of XIGDUO XR in healthy subjects after a standard meal compared to the fasted state resulted in the same extent of exposure for both dapagliflozin and metformin extended-release. Compared to the fasted state, the standard meal resulted in 35% reduction and a delay of 1 to 2 hours in the peak plasma concentrations of dapagliflozin. This effect of food is not considered to be clinically meaningful. Food has no relevant effect on the pharmacokinetics of metformin when administered as XIGDUO XR combination tablets.

Absorption

Dapagliflozin

Following oral administration of dapagliflozin, the maximum plasma concentration (Cmax) is usually attained within 2 hours under fasting state. The Cmax and AUC values increase dose proportionally with increase in dapagliflozin dose in the therapeutic dose range. The absolute oral bioavailability of dapagliflozin following the administration of a 10 mg dose is 78%. Administration of dapagliflozin with a high-fat meal decreases its Cmax by up to 50% and prolongs Tmax by approximately 1 hour but does not alter AUC as compared with the fasted state. These changes are not considered to be clinically meaningful and dapagliflozin can be administered with or without food.

Metformin HCl

Following a single oral dose of metformin HCl extended-release, Cmax is achieved with a median value of 7 hours and a range of 4 to 8 hours. The extent of metformin absorption (as measured by AUC) from the metformin HCl extended-release tablet increased by approximately 50% when given with food. There was no effect of food on Cmax and Tmax of metformin. Metformin HCl extended-release tablets and metformin HCl immediate-release tablets have a similar extent of absorption (as measured by AUC), while peak plasma levels of metformin extended-release tablets are approximately 20% lower than those of metformin immediate-release tablets at the same dose.

Distribution

Dapagliflozin

Dapagliflozin is approximately 91% protein bound. Protein binding is not altered in patients with renal or hepatic impairment.

Metformin HCl

Distribution studies with extended-release metformin have not been conducted; however, the apparent volume of distribution (V/F) of metformin following single oral doses of immediate-release metformin 850 mg averaged 654 ± 358 L. Metformin is negligibly bound to plasma proteins, in contrast to sulfonylureas, which are more than 90% protein bound. Metformin partitions into erythrocytes.

Metabolism

Dapagliflozin

The metabolism of dapagliflozin is primarily mediated by UGT1A9; CYP-mediated metabolism is a minor clearance pathway in humans. Dapagliflozin is extensively metabolized, primarily to yield dapagliflozin 3-O-glucuronide, which is an inactive metabolite. Dapagliflozin 3-O-glucuronide accounted for 61% of a 50 mg [^14C]-dapagliflozin dose and is the predominant drug-related component in human plasma.

Metformin HCl

Intravenous single-dose studies in healthy subjects demonstrate that metformin is excreted unchanged in the urine and does not undergo hepatic metabolism (no metabolites have been identified in humans) or biliary excretion.

Metabolism studies with extended-release metformin tablets have not been conducted.

Elimination

Dapagliflozin

Dapagliflozin and related metabolites are primarily eliminated via the renal pathway. Following a single 50 mg dose of [^14C]-dapagliflozin, 75% and 21% total radioactivity is excreted in urine and feces, respectively. In urine, less than 2% of the dose is excreted as parent drug. In feces, approximately 15% of the dose is excreted as parent drug. The mean plasma terminal half-life (t½) for dapagliflozin is approximately 12.9 hours following a single oral dose of dapagliflozin 10 mg.

Metformin HCl

Renal clearance is approximately 3.5‑times greater than creatinine clearance, which indicates that tubular secretion is the major route of metformin elimination. Following oral administration, approximately 90% of the absorbed drug is eliminated via the renal route within the first 24 hours, with a plasma elimination half-life of approximately 6.2 hours. In blood, the elimination half-life is approximately 17.6 hours, suggesting that the erythrocyte mass may be a compartment of distribution.

Specific Populations

Geriatric Patients

Dapagliflozin

Based on a population pharmacokinetic analysis, age does not have a clinically meaningful effect on systemic exposures of dapagliflozin.

Metformin HCl

Limited data from controlled pharmacokinetic studies of metformin in healthy elderly subjects suggest that total plasma clearance of metformin is decreased, the half-life is prolonged, and Cmax is increased, compared to healthy young subjects. From these data, it appears that the change in metformin pharmacokinetics with aging is primarily accounted for by a change in renal function.

Pediatric Patients

Dapagliflozin

The pharmacokinetics and pharmacodynamics (glucosuria) of dapagliflozin in pediatric patients aged 10 to 17 years with type 2 diabetes mellitus were similar to those observed in adult patients with same renal function.

Metformin HCl

After administration of a single oral metformin 500 mg tablet with food, geometric mean metformin Cmax and AUC differed less than 5% between pediatric type 2 diabetic patients (12-16 years of age) and gender- and weight-matched healthy adults (20-45 years of age), all with normal renal function.

Male and Female Patients

Dapagliflozin

Based on a population pharmacokinetic analysis, gender does not have a clinically meaningful effect on systemic exposures of dapagliflozin.

Metformin HCl

Metformin pharmacokinetic parameters did not differ significantly between healthy subjects and patients with type 2 diabetes mellitus when analyzed according to gender (males=19, females=16). Similarly, in controlled clinical studies in patients with type 2 diabetes mellitus, the antihyperglycemic effect of metformin was comparable in males and females.

Racial or Ethnic Groups

Dapagliflozin

Based on a population pharmacokinetic analysis, race (White, Black or African American, or Asian) does not have a clinically meaningful effect on systemic exposures of dapagliflozin.

Metformin HCl

No studies of metformin pharmacokinetic parameters according to race have been performed. In controlled clinical studies of metformin in patients with type 2 diabetes mellitus, the antihyperglycemic effect was comparable in Whites (n=249), Black or African Americans (n=51), and Hispanic or Latino Ethnicity (n=24).

Patients with Renal Impairment

Dapagliflozin

At steady-state (20 mg once daily dapagliflozin for 7 days), adult patients with type 2 diabetes mellitus with mild, moderate, or severe renal impairment (as determined by eGFR) had geometric mean systemic exposures of dapagliflozin that were 45%, 100% and 200% higher, respectively, as compared to patients with type 2 diabetes mellitus with normal renal function. Higher systemic exposure of dapagliflozin in patients with type 2 diabetes mellitus with renal impairment did not result in a correspondingly higher 24-hour urinary glucose excretion. The steady-state 24-hour urinary glucose excretion in patients with type 2 diabetes mellitus and mild, moderate, and severe renal impairment was 42%, 80%, and 90% lower, respectively, than in patients with type 2 diabetes mellitus with normal renal function. The impact of hemodialysis on dapagliflozin exposure is not known [see Dosage and Administration (2.4), Warnings and Precautions (5.3), Use in Specific Populations (8.6) and Clinical Studies (14)].

Metformin HCl

In patients with decreased renal function, the plasma and blood half-life of metformin is prolonged and the renal clearance is decreased [see Contraindications (4) and Warnings and Precautions (5.1)].

Patients with Hepatic Impairment

Dapagliflozin

In adult patients with mild and moderate hepatic impairment (Child-Pugh classes A and B), mean Cmax and AUC of dapagliflozin were up to 12% and 36% higher, respectively, as compared to healthy matched control subjects following single-dose administration of 10 mg dapagliflozin. These differences were not considered to be clinically meaningful. In adult patients with severe hepatic impairment (Child-Pugh class C), mean Cmax and AUC of dapagliflozin were up to 40% and 67% higher, respectively, as compared to healthy matched controls.

Metformin HCl

No pharmacokinetic studies of metformin have been conducted in patients with hepatic impairment [see Warnings and Precautions (5.1)].

Body Weight

Dapagliflozin

Based on a population pharmacokinetic analysis, body weight does not have a clinically meaningful effect on systemic exposures of dapagliflozin.

Drug Interactions

Specific pharmacokinetic drug interaction studies with XIGDUO XR have not been performed, although such studies have been conducted with the individual dapagliflozin and metformin components.

In Vitro Assessment of Drug Interactions

Dapagliflozin

In in vitro studies, dapagliflozin and dapagliflozin 3-O-glucuronide neither inhibited CYP 1A2, 2C9, 2C19, 2D6, or 3A4, nor induced CYP 1A2, 2B6, or 3A4. Dapagliflozin is a weak substrate of the P-glycoprotein (P‑gp) active transporter, and dapagliflozin 3-O-glucuronide is a substrate for the OAT3 active transporter. Dapagliflozin or dapagliflozin 3-O-glucuronide did not meaningfully inhibit P-gp, OCT2, OAT1, or OAT3 active transporters. Overall, dapagliflozin is unlikely to affect the pharmacokinetics of concurrently administered medications that are P-gp, OCT2, OAT1, or OAT3 substrates.

Effects of Other Drugs on Metformin

Table 7 shows the effect of coadministered drugs on the pharmacokinetics of metformin in adults.

Table 7: Effect of Coadministered Drug on Plasma Metformin Systemic Exposure
Coadministered Drug; (Dose Regimen) [All metformin and coadministered drugs were given as single doses.] | Metformin; (Dose Regimen) | Metformin
Coadministered Drug; (Dose Regimen) [All metformin and coadministered drugs were given as single doses.] | Metformin; (Dose Regimen) | Change [Percent change (with/without coadministered drug and no change = 0%); ↑ and ↓ indicate the exposure increase and decrease, respectively.] in AUC [AUC = AUC(INF).] | Change in Cmax
No dosing adjustments required for the following:
Glyburide (5 mg) | 850 mg | ↓9% [Ratio of arithmetic means.] | ↓7%
Furosemide (40 mg) | 850 mg | ↑15% | ↑22%
Nifedipine (10 mg) | 850 mg | ↑9% | ↑20%
Propranolol (40 mg) | 850 mg | ↓10% | ↓6%
Ibuprofen (400 mg) | 850 mg | ↑5% | ↑7%
Drugs eliminated by renal tubular secretion may increase the accumulation of metformin [see Drug Interactions (7)].
Cimetidine (400 mg) | 850 mg | ↑40% | ↑60%

Effects of Metformin on Other Drugs

Table 8 shows the effect of metformin on the pharmacokinetics of coadministered drugs in adults.

Table 8: Effect of Metformin on Coadministered Drug Systemic Exposure
Coadministered Drug (Dose Regimen) [All metformin and coadministered drugs were given as single doses.] | Metformin (Dose Regimen) | Coadministered Drug
Coadministered Drug (Dose Regimen) [All metformin and coadministered drugs were given as single doses.] | Metformin (Dose Regimen) | Change [Percent change (with/without coadministered drug and no change = 0%); ↑ and ↓ indicate the exposure increase and decrease, respectively.] in AUC [AUC = AUC(INF) unless otherwise noted.] | Change in Cmax
No dosing adjustments required for the following:
Glyburide (5 mg) | 850 mg | ↓22% [Ratio of arithmetic means, p-value of difference <0.05.] | ↓37%
Furosemide (40 mg) | 850 mg | ↓12% | ↓31%
Nifedipine (10 mg) | 850 mg | ↑10% [AUC(0-24 hr) reported.] | ↑8%
Propranolol (40 mg) | 850 mg | ↑1% | ↑2%
Ibuprofen (400 mg) | 850 mg | ↓3% [Ratio of arithmetic means.] | ↑1%
Cimetidine (400 mg) | 850 mg | ↓5% | ↑1%

Effects of Other Drugs on Dapagliflozin

Table 9 shows the effect of coadministered drugs on the pharmacokinetics of dapagliflozin in adults. No dose adjustments are recommended for dapagliflozin.

Table 9: Effects of Coadministered Drugs on Dapagliflozin Systemic Exposure
Coadministered Drug (Dose Regimen) [Single dose unless otherwise noted.] | Dapagliflozin (Dose Regimen) | Dapagliflozin
Coadministered Drug (Dose Regimen) [Single dose unless otherwise noted.] | Dapagliflozin (Dose Regimen) | Change [Percent change (with/without coadministered drug and no change = 0%); ↑ and ↓ indicate the exposure increase and decrease, respectively.] in AUC [AUC = AUC(INF) for drugs given as single dose and AUC = AUC(TAU) for drugs given in multiple doses.] | Change in Cmax
No dosing adjustments required for the following:
Oral Antidiabetic Agents
Metformin (1,000 mg) | 20 mg | ↓1% | ↓7%
Pioglitazone (45 mg) | 50 mg | 0% | ↑9%
Sitagliptin (100 mg) | 20 mg | ↑8% | ↓4%
Glimepiride (4 mg) | 20 mg | ↓1% | ↑1%
Voglibose (0.2 mg three times daily) | 10 mg | ↑1% | ↑4%
Other Medications
Hydrochlorothiazide (25 mg) | 50 mg | ↑7% | ↓1%
Bumetanide (1 mg) | 10 mg once daily for 7 days | ↑5% | ↑8%
Valsartan (320 mg) | 20 mg | ↑2% | ↓12%
Simvastatin (40 mg) | 20 mg | ↓1% | ↓2%
Anti-infective Agent
Rifampin (600 mg once daily for 6 days) | 10 mg | ↓22% | ↓7%
Nonsteroidal Anti-inflammatory Agent
Mefenamic Acid (loading dose of 500 mg followed by 14 doses of 250 mg every 6 hours) | 10 mg | ↑51% | ↑13%

Effects of Dapagliflozin on Other Drugs

Table 10 shows the effect of dapagliflozin on other coadministered drugs in adults. Dapagliflozin did not meaningfully affect the pharmacokinetics of the coadministered drugs.

Table 10: Effects of Dapagliflozin on the Systemic Exposures of Coadministered Drugs
Coadministered Drug (Dose Regimen) [Single dose unless otherwise noted.] | Dapagliflozin (Dose Regimen) | Coadministered Drug
Coadministered Drug (Dose Regimen) [Single dose unless otherwise noted.] | Dapagliflozin (Dose Regimen) | Change [Percent change (with/without coadministered drug and no change = 0%); ↑ and ↓ indicate the exposure increase and decrease, respectively.] in AUC [AUC = AUC(INF) for drugs given as single dose and AUC = AUC(TAU) for drugs given in multiple doses.] | Change in Cmax
No dosing adjustments required for the following:
Oral Antidiabetic Agents
Metformin (1,000 mg) | 20 mg | 0% | ↓5%
Pioglitazone (45 mg) | 50 mg | 0% | ↓7%
Sitagliptin (100 mg) | 20 mg | ↑1% | ↓11%
Glimepiride (4 mg) | 20 mg | ↑13% | ↑4%
Other Medications
Hydrochlorothiazide (25 mg) | 50 mg | ↓1% | ↓5%
Bumetanide (1 mg) | 10 mg once daily for 7 days | ↑13% | ↑13%
Valsartan (320 mg) | 20 mg | ↑5% | ↓6%
Simvastatin (40 mg) | 20 mg | ↑19% | ↓6%
Digoxin (0.25 mg) | 20 mg loading dose then 10 mg once daily for 7 days | 0% | ↓1%
Warfarin (25 mg); S-warfarin R-warfarin | 20 mg loading dose then 10 mg once daily for 7 days | ↑3% ↑6% | ↑7% ↑8%

13 NONCLINICAL TOXICOLOGY

13.1 Carcinogenesis, Mutagenesis, Impairment of Fertility

XIGDUO XR

No animal studies have been conducted with XIGDUO XR to evaluate carcinogenesis, mutagenesis, or impairment of fertility. The following data are based on the findings in the studies with dapagliflozin and metformin individually.

Dapagliflozin

Dapagliflozin did not induce tumors in either mice or rats at any of the doses evaluated in 2-year carcinogenicity studies. Oral doses in mice consisted of 5, 15, and 40 mg/kg/day in males and 2, 10 and 20 mg/kg/day in females, and oral doses in rats were 0.5, 2, and 10 mg/kg/day for both males and females. The highest doses evaluated in mice were approximately 72-times (males) and 105-times (females) the clinical dose of 10 mg per day, based on AUC exposure. In rats, the highest dose was approximately 131-times (males) and 186-times (females) the clinical dose of 10 mg per day, based on AUC exposure.

Dapagliflozin was negative in the Ames mutagenicity assay and was positive in a series of in vitro clastogenicity assays in the presence of S9 activation and at concentrations greater than or equal to 100 μg/mL. Dapagliflozin was negative for clastogenicity in a series of in vivo studies evaluating micronuclei or DNA repair in rats at exposure multiples greater than 2100-times the clinical dose.

There was no carcinogenicity or mutagenicity signal in animal studies, suggesting that dapagliflozin does not represent a genotoxic risk to humans.

Dapagliflozin had no effects on mating, fertility, or early embryonic development in treated male or female rats at exposure multiples less than or equal to 1708-times and 998-times the maximum recommended human dose in males and females, respectively.

Metformin HCl

Long-term carcinogenicity studies have been performed in rats (dosing duration of 104 weeks) and mice (dosing duration of 91 weeks) at doses up to and including 900 and 1,500 mg/kg/day, respectively. These doses are both approximately 4‑times the maximum recommended human dose of 2,000 mg based on body surface area comparisons. No evidence of carcinogenicity with metformin was found in either male or female mice. Similarly, there was no tumorigenic potential observed with metformin in male rats. There was, however, an increased incidence of benign stromal uterine polyps in female rats treated with 900 mg/kg/day.

There was no evidence of a mutagenic potential of metformin in the following in vitro tests: Ames test (S. typhimurium), gene mutation test (mouse lymphoma cells), or chromosomal aberrations test (human lymphocytes). Results in the in vivo mouse micronucleus test were also negative.

Fertility of male or female rats was unaffected by metformin when administered at doses as high as 600 mg/kg/day, which is approximately 3-times the maximum recommended human dose based on body surface area comparisons.

14 CLINICAL STUDIES

14.1 Glycemic Control Trials in Adults with Type 2 Diabetes Mellitus

The effectiveness of XIGDUO XR has been established in clinical trials of the coadministration of oral dapagliflozin and metformin HCl extended‑release tablets in treatment-naive adult patients inadequately controlled on diet and exercise alone. The coadministration of dapagliflozin and metformin HCl immediate‑release or extended‑release tablets has been studied in adult patients with type 2 diabetes mellitus inadequately controlled on metformin HCl and compared with a sulfonylurea (glipizide) in combination with metformin HCl. Treatment with dapagliflozin plus metformin HCl at all doses produced statistically significant improvements in HbA1c and fasting plasma glucose (FPG) compared to placebo in combination with metformin HCl (initial or add-on therapy). HbA1c reductions were seen across subgroups including gender, age, race, duration of disease, and baseline body mass index (BMI).

Dapagliflozin Initial Combination Therapy with Metformin HCl Extended-Release

A total of 1236 treatment-naive adult patients with inadequately controlled type 2 diabetes mellitus (HbA1c ≥7.5% and ≤12%) participated in 2 active-controlled trials of 24-week duration to evaluate initial therapy with dapagliflozin 5 mg (NCT00643851) or 10 mg (NCT00859898) in combination with metformin extended-release formulation.

In one trial, 638 patients randomized to 1 of 3 treatment arms following a 1-week lead-in period received: dapagliflozin 10 mg plus metformin HCl extended-release (up to 2,000 mg/day), dapagliflozin 10 mg plus placebo, or metformin HCl extended-release (up to 2,000 mg/day) plus placebo. Metformin HCl extended-release dosage was up-titrated weekly in 500 mg increments, as tolerated, with a median dosage achieved of 2,000 mg.

The combination treatment of dapagliflozin 10 mg plus metformin HCl extended-release provided statistically significant improvements in HbA1c and FPG compared with either of the monotherapy treatments and statistically significant reduction in body weight compared with metformin HCl extended-release alone (see Table 11 and Figure 2). Dapagliflozin 10 mg as monotherapy also provided statistically significant improvements in FPG and statistically significant reduction in body weight compared with metformin HCl alone and was non-inferior to metformin HCl extended-release monotherapy in lowering HbA1c.

Table 11: Results at Week 24 (LOCF [LOCF: last observation (prior to rescue for rescued patients) carried forward.]) in an Active-Controlled Trial of Dapagliflozin Initial Combination Therapy with Metformin HCl Extended-Release in Adults with Type 2 Diabetes Mellitus
Efficacy Parameter | Dapagliflozin; 10 mg; +; Metformin HCl extended‑release | Dapagliflozin; 10 mg | Metformin HCl extended‑release
 | N=211 [All randomized patients who took at least one dose of double-blind trial medication during the short-term double-blind period.] | N=219 | N=208
HbA1c (%)
Baseline (mean) | 9.1 | 9.0 | 9.0
Change from baseline (adjusted mean [Least squares mean adjusted for baseline value.]) | -2.0 | -1.5 | -1.4
Difference from dapagliflozin (adjusted mean) (95% CI) | -0.5 [p-value <0.0001.]; (-0.7, -0.3)
Difference from metformin HCl extended‑release (adjusted mean) (95% CI) | -0.5; (-0.8, -0.3) | 0.0 [Non-inferior versus metformin HCl extended‑release.]; (-0.2, 0.2)
Percent of patients achieving HbA1c <7% adjusted for baseline | 46.6% | 31.7% | 35.2%
FPG (mg/dL)
Baseline (mean) | 189.6 | 197.5 | 189.9
Change from baseline (adjusted mean) | -60.4 | -46.4 | -34.8
Difference from dapagliflozin (adjusted mean) (95% CI) | -13.9; (-20.9, -7.0)
Difference from metformin HCl extened‑release (adjusted mean) (95% CI) | -25.5; (-32.6, -18.5) | -11.6 [p-value <0.05.]; (-18.6, -4.6)
Body Weight (kg)
Baseline (mean) | 88.6 | 88.5 | 87.2
Change from baseline (adjusted mean) | -3.3 | -2.7 | -1.4
Difference from metformin HCl extended‑release (adjusted mean) (95% CI) | -2.0; (-2.6, -1.3) | -1.4; (-2.0, -0.7)

Figure 2: Adjusted Mean Change from Baseline Over Time in HbA1c (%) in a 24-Week Active-Controlled Trial of Dapagliflozin Initial Combination Therapy with Metformin HCl Extended-Release in Adults with Type 2 Diabetes Mellitus

In the second trial (NCT00643851), 603 patients were randomized to 1 of 3 treatment arms following a 1-week lead-in period: dapagliflozin 5 mg plus metformin HCl extended-release (up to 2,000 mg/day), dapagliflozin 5 mg plus placebo, or metformin HCl extended-release (up to 2,000 mg/day) plus placebo. Metformin HCl extended-release dosage was up-titrated weekly in 500 mg increments, as tolerated, with a median dosage achieved of 2,000 mg.

The combination treatment of dapagliflozin 5 mg plus metformin HCl extended-release provided statistically significant improvements in HbA1c and FPG compared with either of the monotherapy treatments and statistically significant reduction in body weight compared with metformin HCl extended-release alone (see Table 12).

Table 12: Results at Week 24 (LOCF [LOCF: last observation (prior to rescue for rescued patients) carried forward.]) in an Active-Controlled Trial of Dapagliflozin Initial Combination Therapy with Metformin HCl Extended-Release in Adults with Type 2 Diabetes Mellitus
Efficacy Parameter | Dapagliflozin; 5 mg; +; Metformin HCl extended‑release | Dapagliflozin; 5 mg | Metformin HCl extended‑release
 | N=194 [All randomized patients who took at least one dose of double-blind trial medication during the short-term double-blind period.] | N=203 | N=201
HbA1c (%)
Baseline (mean) | 9.2 | 9.1 | 9.1
Change from baseline (adjusted mean [Least squares mean adjusted for baseline value.]) | -2.1 | -1.2 | -1.4
Difference from dapagliflozin (adjusted mean) (95% CI) | -0.9 [p-value <0.0001.]; (-1.1, -0.6)
Difference from metformin HCl extended-release (adjusted mean) (95% CI) | -0.7; (-0.9, -0.5)
Percent of patients achieving HbA1c <7% adjusted for baseline | 52.4% [p-value <0.05.] | 22.5% | 34.6%
FPG (mg/dL)
Baseline (mean) | 193.4 | 190.8 | 196.7
Change from baseline (adjusted mean) | -61.0 | -42.0 | -33.6
Difference from dapagliflozin (adjusted mean) (95% CI) | -19.1; (-26.7, -11.4)
Difference from metformin HCl extended‑release (adjusted mean) (95% CI) | -27.5; (-35.1, -19.8)
Body Weight (kg)
Baseline (mean) | 84.2 | 86.2 | 85.8
Change from baseline (adjusted mean) | -2.7 | -2.6 | -1.3
Difference from metformin HCl extended‑release (adjusted mean) (95% CI) | -1.4; (-2.0, -0.7)

Dapagliflozin Add-On to Metformin HCl Immediate-Release

A total of 546 adult patients with type 2 diabetes mellitus with inadequate glycemic control (HbA1c ≥7% and ≤10%) participated in a 24-week, placebo-controlled trial to evaluate dapagliflozin in combination with metformin HCl (NCT00528879). Patients on metformin HCl at a dosage of at least 1,500 mg/day were randomized after completing a 2-week, single-blind, placebo lead-in period. Following the lead-in period, eligible patients were randomized to dapagliflozin 5 mg, dapagliflozin 10 mg, or placebo in addition to their current dosage of metformin HCl.

As add-on treatment to metformin HCl, dapagliflozin 10 mg provided statistically significant improvements in HbA1c and FPG, and statistically significant reduction in body weight compared with placebo at Week 24 (see Table 13 and Figure 3). Statistically significant (p<0.05 for both dosages) mean changes from baseline in systolic blood pressure relative to placebo plus metformin were −4.5 mmHg and −5.3 mmHg with dapagliflozin 5 mg and 10 mg plus metformin HCl, respectively.

Table 13: Results of a 24-Week (LOCF [LOCF: last observation (prior to rescue for rescued patients) carried forward.]) Placebo-Controlled Trial of Dapagliflozin in Add-On Combination with Metformin HCl Immediate-Release in Adults with Type 2 Diabetes Mellitus
Efficacy Parameter | Dapagliflozin; 10 mg; +; Metformin HCl immediate-; release; N=135 [All randomized patients who took at least one dose of double-blind trial medication during the short-term double-blind period.] | Dapagliflozin; 5 mg; +; Metformin HCl immediate-; release; N=137 | Placebo; +; Metformin HCl immediate-; release; N=137
HbA1c (%)
Baseline (mean) | 7.9 | 8.2 | 8.1
Change from baseline (adjusted mean [Least squares mean adjusted for baseline value.]) | -0.8 | -0.7 | -0.3
Difference from placebo (adjusted mean) (95% CI) | -0.5 [p-value <0.0001 versus placebo + metformin HCl.]; (-0.7, -0.3) | -0.4; (-0.6, -0.2)
Percent of patients achieving HbA1c <7% adjusted for baseline | 40.6% [p-value <0.05 versus placebo + metformin HCl.] | 37.5% | 25.9%
FPG (mg/dL)
Baseline (mean) | 156.0 | 169.2 | 165.6
Change from baseline at Week 24 (adjusted mean) | -23.5 | -21.5 | -6.0
Difference from placebo (adjusted mean) (95% CI) | -17.5; (-25.0, -10.0) | -15.5; (-22.9, -8.1)
Change from baseline at Week 1; (adjusted mean) | -16.5; (N=115) | -12.0; (N=121) | 1.2 (N=126)
Body Weight (kg)
Baseline (mean) | 86.3 | 84.7 | 87.7
Change from baseline (adjusted mean) | -2.9 | -3.0 | -0.9
Difference from placebo (adjusted mean) (95% CI) | -2.0; (-2.6, -1.3) | -2.2; (-2.8, -1.5)

Figure 3: Adjusted Mean Change from Baseline Over Time in HbA1c (%) in a 24-Week Placebo-Controlled Trial of Dapagliflozin in Combination with Metformin HCl Immediate-Release in Adults with Type 2 Diabetes Mellitus

Active Glipizide-Controlled Trial of Dapagliflozin as Add-On to Metformin HCl Immediate-Release in Adults with Type 2 Diabetes Mellitus

A total of 816 adult patients with type 2 diabetes mellitus with inadequate glycemic control (HbA1c >6.5% and ≤10%) were randomized in a 52-week, glipizide-controlled, non-inferiority trial to evaluate dapagliflozin as add-on therapy to metformin HCl (NCT00660907). Patients on metformin HCl at a dosage of at least 1,500 mg/day were randomized following a 2-week placebo lead-in period to glipizide or dapagliflozin (5 mg or 2.5 mg, respectively) and were up-titrated over 18 weeks to optimal glycemic effect (FPG <110 mg/dL, <6.1 mmol/L) or to the highest dose level (up to glipizide 20 mg and dapagliflozin 10 mg) as tolerated by patients. Thereafter, dosages were kept constant, except for down-titration to prevent hypoglycemia.

At the end of the titration period, 87% of patients treated with dapagliflozin had been titrated to the maximum trial dosage (10 mg) versus 73% treated with glipizide (20 mg). Dapagliflozin treatment led to a similar mean reduction in HbA1c from baseline at Week 52 (LOCF), compared with glipizide, thus demonstrating non-inferiority (see Table 14). Dapagliflozin treatment led to a statistically significant mean reduction in body weight from baseline at Week 52 (LOCF) compared with a mean increase in body weight in the glipizide group. Statistically significant (p<0.0001) mean change from baseline in systolic blood pressure relative to glipizide plus metformin was -5.0 mmHg with dapagliflozin plus metformin.

Table 14: Results at Week 52 (LOCF [LOCF: last observation carried forward.]) in an Active-Controlled Trial Comparing Dapagliflozin to Glipizide as Add-On to Metformin in Adults with Type 2 Diabetes Mellitus
Efficacy Parameter | Dapagliflozin; +; Metformin HCl; immediate‑release; N=400 [Randomized and treated patients with baseline and at least 1 post-baseline efficacy measurement.] | Glipizide; +; Metformin HCl; immediate‑release; N=401
HbA1c (%)
Baseline (mean) | 7.7 | 7.7
Change from baseline (adjusted mean [Least squares mean adjusted for baseline value.]) | -0.5 | -0.5
Difference from glipizide + metformin HCl immediate‑release (adjusted mean); (95% CI) | 0.0 [Noninferior to glipizide + metformin HCl.]; (-0.1, 0.1)
Body Weight (kg)
Baseline (mean) | 88.4 | 87.6
Change from baseline (adjusted mean) | -3.2 | 1.4
Difference from glipizide + metformin HCl immediate‑release (adjusted mean); (95% CI) | -4.7 [p-value <0.0001.]; (-5.1, -4.2)

Use in Adults with Type 2 Diabetes Mellitus and Moderate Renal Impairment

Dapagliflozin was assessed in two placebo-controlled trials of adult patients with type 2 diabetes mellitus and moderate renal impairment.

Patients with type 2 diabetes mellitus and an eGFR between 45 to less than 60 mL/min/1.73 m2 inadequately controlled on current diabetes therapy participated in a 24-week, double-blind, placebo-controlled clinical trial (NCT02413398). Patients were randomized to either dapagliflozin 10 mg or placebo, administered orally once daily. At Week 24, dapagliflozin provided statistically significant reductions in HbA1c compared with placebo (Table 15).

Table 15: Results at Week 24 of Placebo-Controlled Trial for Dapagliflozin in Adults with Type 2 Diabetes Mellitus and Renal Impairment (eGFR 45 to less than 60 mL/min/1.73 m^2)
 | Dapagliflozin 10 mg | Placebo
Number of patients: | N=160 | N=161
HbA1c (%)
Baseline (mean) | 8.3 | 8.0
Change from baseline (adjusted mean [Least squares mean adjusted for baseline value; at Week 24, HbA1c was missing for 5.6% and 6.8% of individuals treated with dapagliflozin and placebo, respectively. Retrieved dropouts, i.e., observed HbA1c at Week 24 from subjects who discontinued treatment, were used to impute missing values in HbA1c.]) | -0.4 | -0.1
Difference from placebo (adjusted mean); (95% CI) | -0.3 [p-value =0.008 versus placebo.]; (-0.5, - 0.1)

14.2 Glycemic Control in Pediatric Patients Aged 10 Years and Older with Type 2 Diabetes Mellitus

Glycemic Control Trial of Dapagliflozin in Pediatric Patients Aged 10 to 17 Years with Type 2 Diabetes Mellitus

In a pediatric trial (NCT03199053), patients aged 10 to 17 years with inadequately controlled type 2 diabetes mellitus (HbA1c ≥6.5% and ≤10.5%) were randomized to dapagliflozin (81 patients) or placebo (76 patients) as add-on to metformin HCl, insulin or a combination of metformin HCl and insulin. In this 26-week, placebo-controlled, double-blind randomized clinical trial with a 26‑week safety extension, patients received 5 mg of dapagliflozin or placebo following a lead-in period. At Week 14, patients with HbA1c values <7% remained on 5 mg while patients with HbA1c values ≥7% were randomized to either continue on 5 mg or up‑titrate to 10 mg.

At baseline, 88% of dapagliflozin-treated patients and 89% of placebo-treated patients were on metformin HCl with or without insulin as background medication. The mean HbA1c at baseline was 8.2% in dapagliflozin-treated patients and 8.0% in placebo-treated patients, and the mean duration of type 2 diabetes mellitus was 2.3 years in dapagliflozin-treated patients and 2.5 years in placebo-treated patients. The mean age was 14.4 years in dapagliflozin-treated patients and 14.7 years in placebo-treated patients, and approximately 61% of dapagliflozin-treated patients and 58% of placebo-treated patients were female. In dapagliflozin-treated patients, approximately 52% were White, 22% were Asian, 9% were Black or African American, and 56% were of Hispanic or Latino ethnicity. In placebo-treated patients, approximately 42% were White, 32% were Asian, 4% were Black or African American, and 45% were of Hispanic or Latino ethnicity. The mean BMI was 29.7 kg/m2 in dapagliflozin-treated patients and 28.5 kg/m2 in placebo-treated patients, and mean BMI Z-score was 1.7 in dapagliflozin-treated patients and 1.5 in placebo-treated patients. The mean eGFR at baseline was 115 mL/min/1.73 m2 in dapagliflozin-treated patients and 113 mL/min/1.73 m^2 in placebo-treated patients.

At Week 26, treatment with dapagliflozin provided statistically significant improvements in HbA1c compared with placebo (Table 16). This effect was consistent across subgroups including race, ethnicity, sex, age group (≥10 to <15 years of age and ≥15 to <18 years of age), background antidiabetic treatment, and baseline BMI.

The treatment benefit with dapagliflozin was consistent in the subgroup of patients with metformin HCl with or without insulin as background therapy [adjusted mean change in HbA1c relative to placebo from baseline to Week 26 was -1.0% (95% CI -1.6, -0.4)].

Table 16: Results at Week 26 in a Placebo-Controlled Trial of Dapagliflozin as Add-On to Metformin HCl and/or Insulin in Pediatric Patients Aged 10 Years and Older with Type 2 Diabetes Mellitus
Efficacy Parameter | Dapagliflozin 5 mg and 10 mg | Placebo
Intent-to-Treat Population (N) [All randomized patients who received at least one dose of double-blind trial medication during the treatment period. Includes data regardless of rescue or premature treatment discontinuation.] | 81 | 76
HbA1c [Multiple imputations using placebo washout approach for missing efficacy endpoint. Imputed for HbA1c (dapagliflozin N=6 (7.4%), placebo N=6 (7.9%)), for FPG (dapagliflozin N=6 (7.4%), placebo N=8 (10.5%)).] (%)
Baseline (mean) | 8.2 | 8.0
Change from baseline (adjusted mean [Least squares mean adjusted for baseline value, treatment, age, gender and baseline diabetic medication.]) | -0.6 | 0.4
Difference from placebo (adjusted mean) (95% CI) | -1.0 [p-value versus placebo <0.001. p-value is two-sided.]; (-1.6, -0.5)
FPG (mg/dL)
Baseline (mean) | 162.2 | 152.0
Change from baseline (adjusted mean) | -10.3 | 9.2
Difference from placebo (adjusted mean) (95% CI) | -19.5 [p-value versus placebo <0.05. p-value is two-sided.]; (-36.4, -2.6)
Percent of Subjects Achieving a HbA1c Level <7% | 34.6% | 25.0%
CI=confidence interval

Glycemic Control Trial of Metformin HCl Immediate-Release in Pediatric Patients Aged 10 to 16 Years with Type 2 Diabetes Mellitus

A double-blind, placebo-controlled trial was conducted in pediatric patients aged 10 to 16 years with type 2 diabetes mellitus (mean FPG 182.2 mg/dL), where patients were treated with metformin HCl immediate-release tablets (up to 2,000 mg/day) for up to 16 weeks (mean duration of treatment 11 weeks). The results are displayed in Table 17.

Table 17: Mean Change in Fasting Plasma Glucose at Week 16 Comparing Metformin HCl vs. Placebo in Pediatric Patients [Pediatric patients mean age 13.8 years (range 10-16 years)] with Type 2 Diabetes Mellitus
 | Metformin HCl | Placebo | p-value
FPG; Baseline; Change at Final Visit | (n=37); 162.4; -42.9 | (n=36); 192.3; 21.4 | <0.001

Mean baseline body weight was 205 lbs and 189 lbs in the metformin HCl immediate-release and placebo arms, respectively. Mean change in body weight from baseline to week 16 was -3.3 lbs and -2.0 lbs in the metformin HCl and placebo arms, respectively.

14.3 Cardiovascular Outcomes in Adults with Type 2 Diabetes Mellitus

Dapagliflozin Effect on Cardiovascular Events (DECLARE, NCT01730534) was an international, multicenter, randomized, double-blind, placebo-controlled, clinical trial conducted to determine the effect of dapagliflozin 10 mg relative to placebo on cardiovascular (CV) outcomes when added to current background therapy. All patients had type 2 diabetes mellitus and either established CV disease or two or more additional CV risk factors (age ≥55 years in men or ≥60 years in women and one or more of dyslipidemia, hypertension, or current tobacco use). Concomitant antidiabetic and atherosclerotic therapies could be adjusted, at the discretion of investigators, to ensure participants were treated according to the standard care for these diseases.

Of 17160 randomized patients, 6974 (40.6%) had established CV disease and 10186 (59.4%) did not have established CV disease. A total of 8582 patients were randomized to dapagliflozin 10 mg, 8578 to placebo, and patients were followed for a median of 4.2 years.

Approximately 80% of the trial population was White, 4% Black or African American, and 13% Asian. The mean age was 64 years, and approximately 63% were male.

Mean duration of diabetes was 11.9 years and 22.4% of patients had diabetes for less than 5 years. Mean eGFR was 85.2 mL/min/1.73 m^2. At baseline, 23.5% of patients had microalbuminuria (UACR ≥30 to ≤300 mg/g) and 6.8% had macroalbuminuria (UACR >300 mg/g). Mean HbA1c was 8.3% and mean BMI was 32.1 kg/m^2. At baseline, 10% of patients had a history of heart failure.

Most patients (98.1%) used one or more antihyperglycemic medications at baseline. 82.0% of the patients were being treated with metformin HCl, 40.9% with insulin, 42.7% with a sulfonylurea, 16.8% with a DPP4 inhibitor, and 4.4% with a GLP-1 receptor agonist.

Approximately 81.3% of patients were treated with angiotensin converting enzyme inhibitors or angiotensin receptor blockers, 75.0% with statins, 61.1% with antiplatelet therapy, 55.5% with acetylsalicylic acid, 52.6% with beta-blockers, 34.9% with calcium channel blockers, 22.0% with thiazide diuretics, and 10.5% with loop diuretics.

A Cox proportional hazards model was used to test for non-inferiority against the pre-specified risk margin of 1.3 for the hazard ratio (HR) of the composite of CV death, myocardial infarction (MI), or ischemic stroke (MACE) and if non-inferiority was demonstrated, to test for superiority on the two primary endpoints: 1) the composite of hospitalization for heart failure or CV death, and 2) MACE.

The incidence rate of MACE was similar in both treatment arms: 2.30 MACE events per 100 patient-years on dapagliflozin vs 2.46 MACE events per 100 patient-years on placebo. The estimated hazard ratio of MACE associated with dapagliflozin relative to placebo was 0.93 with a 95% CI of (0.84, 1.03). The upper bound of this confidence interval, 1.03, excluded the pre-specified non-inferiority margin of 1.3.

Dapagliflozin 10 mg was superior to placebo in reducing the incidence of the primary composite endpoint of hospitalization for heart failure or CV death [HR 0.83 (95% CI 0.73, 0.95)].

The treatment effect was due to a significant reduction in the risk of hospitalization for heart failure in subjects randomized to dapagliflozin 10 mg [HR 0.73 (95% CI 0.61, 0.88)], with no change in the risk of CV death (Table 18 and Figures 4 and 5).

Table 18: Treatment Effects for the Primary Endpoints* and their Components* in the DECLARE Trial
 | Patients with events n(%)
Efficacy Variable (time to first occurrence) | Dapagliflozin 10 mg N=8582 | Placebo N=8578 | Hazard Ratio (95% CI)
Primary Endpoints
Composite of Hospitalization for Heart Failure, CV Death† | 417 (4.9) | 496 (5.8) | 0.83 (0.73, 0.95)
Composite Endpoint of CV Death, MI, Ischemic Stroke | 756 (8.8) | 803 (9.4) | 0.93 (0.84, 1.03)
Components of the composite endpoints‡
Hospitalization for Heart Failure | 212 (2.5) | 286 (3.3) | 0.73 (0.61, 0.88)
CV Death | 245 (2.9) | 249 (2.9) | 0.98 (0.82, 1.17)
Myocardial Infarction | 393 (4.6) | 441 (5.1) | 0.89 (0.77, 1.01)
Ischemic Stroke | 235 (2.7) | 231 (2.7) | 1.01 (0.84, 1.21)
N=Number of patients, CI=Confidence interval, CV=Cardiovascular, MI=Myocardial infarction, eGFR=estimated glomerular filtration rate, ESRD=End‑stage renal disease
* Full analysis set.
† p-value =0.005 versus placebo.
‡ Total number of events presented for each component of the composite endpoints.

Figure 4: Time to First Occurrence of Hospitalization for Heart Failure or CV Death in the DECLARE Trial

Figure 5: Time to First Occurrence of Hospitalization for Heart Failure in the DECLARE Trial

14.4 Chronic Kidney Disease

The Trial to Evaluate the Effect of Dapagliflozin on Renal Outcomes and Cardiovascular Mortality in Patients with Chronic Kidney Disease (DAPA-CKD, NCT03036150) was an international, multicenter, randomized, double-blind, placebo-controlled trial in adult patients with chronic kidney disease (CKD) (eGFR between 25 and 75 mL/min/1.73 m^2) and albuminuria [urine albumin creatinine ratio (UACR) between 200 and 5000 mg/g] who were receiving standard of care background therapy, including a maximally tolerated, labeled daily dosage of an angiotensin-converting enzyme inhibitor (ACEi) or angiotensin receptor blocker (ARB). The trial excluded patients with autosomal dominant or autosomal recessive polycystic kidney disease, lupus nephritis, or ANCA-associated vasculitis and patients requiring cytotoxic, immunosuppressive, or immunomodulatory therapies in the preceding 6 months.

The primary objective was to determine whether dapagliflozin 10 mg reduces the incidence of the composite endpoint of ≥50% sustained decline in eGFR, progression to end stage kidney disease (ESKD) (defined as sustained eGFR<15 mL/min/1.73 m^2, initiation of chronic dialysis treatment or renal transplant), CV or renal death.

A total of 4304 patients were randomized equally to dapagliflozin 10 mg or placebo and were followed for a median of 28.5 months. The trial included patients with type 2 diabetes mellitus (n=2906) and patients without diabetes (n=1398). The mean age of the trial population was 62 years and 67% were male. The population was 53% White, 4% Black or African American, and 34% Asian; 25% were of Hispanic or Latino ethnicity. At baseline, mean eGFR was 43 mL/min/1.73 m^2, 44% of patients had an eGFR 30 mL/min/1.73m^2 to less than 45 mL/min/1.73m^2, and 15% of patients had an eGFR less than 30 mL/min/1.73m^2. Median UACR was 950 mg/g. The most common etiologies of CKD were diabetic nephropathy (58%), ischemic/hypertensive nephropathy (16%), and IgA nephropathy (6%). At baseline, 97% of patients were treated with ACEi or ARB. Approximately 44% were taking antiplatelet agents, and 65% were on a statin.

Out of 2906 (68%) patients who had type 2 diabetes mellitus at randomization, 1455 patients received dapagliflozin 10 mg and 1451 received placebo. At baseline of the patients with type 2 diabetes mellitus, 43% were being treated with metformin HCl (631 patients on dapagliflozin 10 mg and 613 on placebo) and 55% were treated with insulin.

The mean age of the type 2 diabetes mellitus trial population was 64 years, 67% were male, 53% White, 5% Black or African American and 32% Asian, 27% were of Hispanic or Latino ethnicity. In these patients, mean eGFR was 44 mL/min/1.73 m^2, 43% of patients had an eGFR 30 mL/min/1.73 m^2 to below 45 mL/min/1.73 m2, and 14% of patients had an eGFR below 30 mL/min/1.73 m^2. Median UACR was 1017 mg/g. The most common etiologies of CKD in this group were diabetic nephropathy (86%) and ischemic/hypertensive nephropathy (7%).

Dapagliflozin 10 mg reduced the incidence of the primary composite endpoint of ≥50% sustained decline in eGFR, progression to ESKD, CV or renal death in overall population [HR 0.61 (95% CI 0.51,0.72); p<0.0001]. The dapagliflozin 10 mg and placebo event curves separate by Month 4 and continue to diverge over the trial period. The treatment effect reflected a reduction in ≥50% sustained decline in eGFR, progression to ESKD, and CV death. There were few renal deaths during the trial (Table 19 and Figure 6).

The treatment benefit of dapagliflozin 10 mg was consistent in reducing the incidence of the primary composite endpoint in patients with type 2 diabetes mellitus [HR 0.64 (95% CI 0.52, 0.79)] and in patients with type 2 diabetes mellitus and metformin HCl as background therapy [HR 0.74 (95% CI 0.53, 1.03)].

The treatment benefit of dapagliflozin 10 mg was consistent in reducing the incidence of the composite endpoint of CV death or hospitalization for heart failure and all-cause mortality in patients with type 2 diabetes mellitus [HR 0.70 (95% CI 0.53, 0.92) and HR 0.74 (95% CI 0.56, 0.98), respectively] and in patients with type 2 diabetes mellitus and metformin HCl as background therapy [HR 0.59 (95% CI 0.38, 0.91) and HR 0.71 (95% CI 0.46, 1.10)].

Table 19: Treatment Effect for the Primary Composite Endpoint, its Components, and Secondary Composite Endpoints in DAPA CKD Trial
 | Patients with events (event rate)
Efficacy Variable; (time to first occurrence) | Dapagliflozin 10 mg N=2152 | Placebo N=2152 | Hazard ratio (95% CI) | p-value
Composite of ≥50% sustained eGFR decline, ESKD, CV or renal death | 197 (4.6) | 312 (7.5) | 0.61 (0.51, 0.72) | <0.0001
Components of the primary composite endpoint
≥50%Sustained eGFR Decline | 112 (2.6) | 201 (4.8) | 0.53 (0.42, 0.67)
ESKD* | 109 (2.5) | 161 (3.8) | 0.64 (0.50, 0.82)
CV Death | 65 (1.4) | 80 (1.7) | 0.81 (0.58, 1.12)
Renal Death | 2 (<0.1) | 6 (0.1)
≥50% sustained eGFR decline, ESKD or renal death | 142 (3.3) | 243 (5.8) | 0.56 (0.45, 0.68) | <0.0001
CV death or Hospitalization for Heart Failure | 100 (2.2) | 138 (3.0) | 0.71 (0.55, 0.92) | 0.0089
Hospitalization for Heart Failure | 37 (0.8) | 71 (1.6) | 0.51 (0.34, 0.76)
All-Cause Mortality | 101 (2.2) | 146 (3.1) | 0.69 (0.53, 0.88) | 0.0035
N=Number of patients, CI=Confidence interval, CV=Cardiovascular.
* ESKD is defined as sustained eGFR<15 mL/min/1.73 m^2, initiation of chronic dialysis treatment, or transplant.
NOTE: Time to first event was analyzed in a Cox proportional hazards model. Event rates are presented as the number of subjects with event per 100 patient years of follow-up.
There were too few events of renal death to compute a reliable hazard ratio.

Figure 6: Time to First Occurrence of the Primary Composite Endpoint, ≥50% Sustained Decline in eGFR, ESKD, CV or Renal Death (DAPA-CKD Trial)

DAPA-CKD enrolled a population with relatively advanced CKD at high risk of progression. Exploratory analyses of a randomized, double-blind, placebo-controlled trial conducted to determine the effect of dapagliflozin 10 mg on CV outcomes (the DECLARE trial) support the conclusion that dapagliflozin 10 mg is also likely to be effective in patients with less advanced CKD.

14.5 Heart Failure

The efficacy and safety of dapagliflozin 10 mg were assessed independently in two Phase 3 trials in patients with heart failure.

Dapagliflozin And Prevention of Adverse outcomes in Heart Failure (DAPA-HF, NCT03036124) was an international, multicenter, randomized, double-blind, placebo-controlled trial in adult patients with heart failure [New York Heart Association (NYHA) functional class II-IV] with reduced ejection fraction [left ventricular ejection fraction (LVEF) 40% or less] to determine whether dapagliflozin reduces the risk of cardiovascular death and hospitalization for heart failure. Of 4744 patients, 2373 were randomized to dapagliflozin 10 mg and 2371 to placebo and were followed for a median of 18 months. The trial included patients with type 2 diabetes mellitus (n=2139) and patients without diabetes (n=2605).

Dapagliflozin Evaluation to Improve the LIVEs of Patients with PReserved Ejection Fraction Heart Failure (DELIVER, NCT03619213) was an international, multicenter, randomized, double-blind, placebo-controlled trial in patients aged ≥40 years with heart failure (NYHA class II-IV) with LVEF >40% and evidence of structural heart disease to determine whether dapagliflozin reduces the risk of cardiovascular death, hospitalization for heart failure or urgent heart failure visits. Of 6263 patients, 3131 were randomized to dapagliflozin 10 mg and 3132 to placebo and were followed for a median of 28 months. The trial included 654 (10%) heart failure patients who were randomized during hospitalization for heart failure or within 30 days of discharge. The trial included patients with type 2 diabetes mellitus (n=2806) and patients without diabetes (n=3457).

In DAPA-HF, at baseline, 94% of patients were treated with ACEi, ARB or angiotensin receptor-neprilysin inhibitor (ARNI, including sacubitril/valsartan 11%), 96% with beta-blocker, 71% with mineralocorticoid receptor antagonist (MRA), 93% with diuretic, and 26% had an implantable device (with defibrillator function). History of type 2 diabetes mellitus was present in 42%, and an additional 3% had type 2 diabetes mellitus based on a HbA1c ≥6.5% at both enrollment and randomization, totaling to 1075 patients in the dapagliflozin group and 1064 in the placebo group. At baseline of the patients with type 2 diabetes mellitus, 48% were treated with metformin HCl (505 patients on dapagliflozin 10 mg and 515 on placebo) and 25% were treated with insulin.

In DAPA-HF, the mean age of the type 2 diabetes mellitus population was 67 years, 78% were male, 70% White, 6% Black or African American and 23% Asian. At baseline, 64% patients were classified as NYHA class II, 35% class III and 1% class IV, median LVEF was 32%. Patients were on standard of care therapy; 93% of type 2 diabetes mellitus patients were treated with ACEi, ARB, or ARNI (11%), 97% with beta-blocker, 71% with MRA, 95% with diuretic and 27% had an implantable device (with defibrillator function). In these patients, mean eGFR was 63 mL/min/1.73 m2.

In DELIVER, at baseline, 77% of patients were treated with ACEi, ARB or ARNI, 83% with beta-blocker, 43% with MRA and 98% with diuretic. History of type 2 diabetes mellitus was present in 45% of the patients. At baseline of the patients with type 2 diabetes mellitus, 58% were treated with metformin HCl (809 patients on dapagliflozin 10 mg and 832 on placebo) and 30% were treated with insulin.

In DELIVER, the mean age of the type 2 diabetes mellitus population was 71 years, 58% were male, 73% White, 3% Black or African American and 18% Asian. At baseline, 74% patients were classified as NYHA class II, 26% class III and 0.4% class IV, 35% of the patients had LVEF ≤49%, 36% had LVEF 50-59% and 29% had LVEF ≥60%. In the type 2 diabetes mellitus population, 80% were treated with ACEi, ARB or ARNI, 84% with beta-blocker, 40% with MRA, and 98% with diuretic. In these patients, mean eGFR was 59 mL/min/1.73 m^2.

In both trials, dapagliflozin reduced the incidence of the primary composite endpoint of CV death, hospitalization for heart failure or urgent heart failure visit in the overall population (see Table 20). All three components of the primary composite endpoint individually contributed to the treatment effect. In both trials, the dapagliflozin and placebo event curves separated early and continued to diverge over the trial period (see Figure 7).

Table 20: Treatment Effect for the Primary Composite Endpoint* and its Components* in the DAPA-HF and DELIVER Trials (Overall Population)
 | DAPA-HF Trial |  |  |  | DELIVER Trial
 | Patients with events (event rate) |  | Hazard ratio (95% CI) | p-value† | Patients with events (event rate) |  | Hazard ratio (95% CI) | p-value†
Efficacy Variable (Time to first occurrence) | Dapa-gliflozin 10 mg N=2373 | Placebo N=2371 |  |  | Dapa-gliflozin 10 mg N=3131 | Placebo N=3132
Composite of Hospitalization for Heart Failure, CV Death‡ or Urgent Heart Failure Visit | 386 (11.6) | 502 (15.6) | 0.74 (0.65, 0.85) | <0.0001 | 512 (7.8) | 610 (9.6) | 0.82 (0.73, 0.92) | 0.0008
Components of the composite endpoints
CV Death‡ | 227 (6.5) | 273 (7.9) | 0.82 (0.69, 0.98) |  | 231 (3.3) | 261 (3.8) | 0.88 (0.74, 1.05)
Hospitalization for Heart Failure or Urgent Heart Failure Visit | 237 (7.1) | 326 (10.1) | 0.70 (0.59, 0.83) |  | 368 (5.6) | 455 (7.2) | 0.79 (0.69, 0.91)
Hospitalization for Heart Failure | 231 (6.9) | 318 (9.8) | 0.70 (0.59, 0.83) |  | 329 (5.0) | 418 (6.5) | 0.77 (0.67, 0.89)
Urgent Heart Failure Visit | 10 (0.3) | 23 (0.7) | 0.43 (0.20, 0.90) |  | 60 (0.9) | 78 (1.1) | 0.76 (0.55, 1.07)
N=Number of patients, CI=Confidence interval, CV=Cardiovascular.
* Full analysis set.
† Two-sided p-values.
‡ In DAPA-HF, the CV death component of the primary endpoint included death of undetermined cause. In DELIVER, the CV death component of the primary endpoint excluded death of undetermined cause.
NOTE: Time to first event was analyzed in a Cox proportional hazards model. The number of first events for the single components are the actual number of first events for each component and does not add up to the number of events in the composite endpoint. Event rates are presented as the number of subjects with event per 100 patient years of follow-up.

Figure 7: Time to the First Occurrence of the Composite of Cardiovascular Death*, Hospitalization for Heart Failure or Urgent Heart Failure Visit

A) DAPA-HF Trial

B) DELIVER Trial

NOTE: An urgent heart failure visit was defined as an urgent, unplanned, assessment by a physician, e.g., in an Emergency Department, and requiring treatment for worsening heart failure (other than just an increase in oral diuretics).

* In DAPA-HF, the CV death component of the primary endpoint included death of undetermined cause. In DELIVER, the CV death component of the primary endpoint excluded death of undetermined cause.

† Patients at risk is the number of patients at risk at the beginning of the period.

HR=Hazard ratio, CI=Confidence interval, CV=Cardiovascular.

The treatment effect of dapagliflozin on the composite endpoint of cardiovascular death, hospitalization for heart failure or urgent heart failure was consistent across the LVEF range as evaluated in DAPA-HF and DELIVER trials (Figure 8).

Figure 8: Treatment Effects for Primary Composite Endpoint (Cardiovascular Death and Heart Failure Events) by LVEF (DAPA-HF and DELIVER Trials)

* 1 patient in DAPA-HF trial had LVEF >40. 4 patients in DELIVER trial had LVEF ≤40.

In DAPA-HF trial, the 5% and 95% percentiles of LVEF were 20 and 40 respectively. In DELIVER trial, the 5% and 95% percentiles of LVEF were 42 and 70, respectively.

In DAPA-HF, the treatment benefit of dapagliflozin 10 mg in reducing the incidence of the primary composite endpoint was consistent in patients with type 2 diabetes mellitus [HR 0.75 (95% CI 0.63, 0.90)], and in patients with type 2 diabetes mellitus and metformin HCl as background therapy [HR 0.67 (95% CI 0.51, 0.88)].

In DELIVER, the treatment benefit of dapagliflozin 10 mg in reducing the incidence of the primary composite endpoint was consistent in patients with type 2 diabetes mellitus [HR 0.83 (95% CI 0.70, 0.97)].

In DELIVER, the hazard ratio of treatment benefit of dapagliflozin 10 mg in reducing the incidence of the primary composite endpoint in patients with type 2 diabetes mellitus and metformin HCl as background therapy was 0.90 (95% CI 0.72, 1.12).

16 HOW SUPPLIED/STORAGE AND HANDLING

How Supplied

XIGDUO® XR (dapagliflozin and metformin HCl extended-release) tablets have markings on one side, are plain on the reverse side, and are available in the strengths and packages listed in Table 21.

Table 21: XIGDUO XR Tablet Presentations
Tablet Strength | Film-Coated Tablet Color/Shape | Tablet Markings | Pack Size | NDC Code
2.5 mg/ 1,000 mg | Light brown to brown, biconvex, oval-shaped | "1074" and "2.5/1000" debossed on one side and plain on the reverse side | Bottle of 60 | 0310-6225-60
5 mg/ 500 mg | orange, biconvex, capsule-shaped | "1070" and "5/500" debossed on one side and plain on the reverse side | Bottle of 30 | 0310-6250-30
5 mg/ 1,000 mg | pink to dark pink, biconvex, oval-shaped | "1071" and "5/1000" debossed on one side and plain on the reverse side | Bottle of 60 | 0310-6260-60
10 mg/ 500 mg | pink, biconvex, capsule-shaped | "1072" and "10/500" debossed on one side and plain on the reverse side | Bottle of 30 | 0310-6270-30
10 mg/ 1,000 mg | yellow to dark yellow, biconvex, oval-shaped | "1073" and "10/1000" debossed on one side and plain on the reverse side | Bottle of 30 | 0310-6280-30

Storage and Handling

Store at 20°C to 25°C (68°F to 77°F); excursions permitted between 15°C and 30°C (59°F and 86°F) [see USP Controlled Room Temperature].

17 PATIENT COUNSELING INFORMATION

Advise the patient to read the FDA-approved patient labeling (Medication Guide).

Lactic Acidosis

Inform patients of the risks of lactic acidosis due to the metformin component and its symptoms and conditions that predispose to its development [see Warnings and Precautions (5.1)]. Advise patients to discontinue XIGDUO XR immediately and to promptly notify their healthcare provider if unexplained hyperventilation, myalgia, malaise, unusual somnolence, dizziness, slow or irregular heartbeat, sensation of feeling cold (especially in the extremities), or other non-specific symptoms occur. Gastrointestinal symptoms are common during initiation of metformin treatment and may occur during initiation of XIGDUO XR therapy; however, inform patients to consult their physician if they develop unexplained symptoms. Although gastrointestinal symptoms that occur after stabilization are unlikely to be drug related, such an occurrence of symptoms should be evaluated to determine if it may be due to lactic acidosis or other serious disease.

Counsel patients against excessive alcohol intake while receiving XIGDUO XR [see Warnings and Precautions (5.1)].

Inform patients about the importance of regular testing of renal function and hematological parameters when receiving treatment with XIGDUO XR [see Contraindications (4) and Warnings and Precautions (5.1)].

Instruct patients to inform their healthcare provider that they are taking XIGDUO XR prior to any surgical or radiological procedure, as temporary discontinuation of XIGDUO XR may be required until renal function has been confirmed to be normal [see Warnings and Precautions (5.1)].

Diabetic Ketoacidosis in Patients with Type 1 Diabetes Mellitus and Other Ketoacidosis

Inform patients that XIGDUO XR can cause potentially fatal ketoacidosis and that type 2 diabetes mellitus and pancreatic disorders (e.g., history of pancreatitis or pancreatic surgery) are risk factors.

Educate all patients on precipitating factors (such as insulin dose reduction or missed insulin doses, infection, reduced caloric intake, ketogenic diet, surgery, dehydration, and alcohol abuse) and symptoms of ketoacidosis (including nausea, vomiting, abdominal pain, tiredness, and labored breathing). Inform patients that blood glucose may be normal even in the presence of ketoacidosis.

Advise patients that they may be asked to monitor ketones. If symptoms of ketoacidosis occur, instruct patients to discontinue XIGDUO XR and seek medical attention immediately [see Warnings and Precautions (5.2)].

Volume Depletion

Inform patients that symptomatic hypotension may occur with XIGDUO XR and advise them to contact their healthcare provider if they experience such symptoms [see Warnings and Precautions (5.3)]. Inform patients that dehydration may increase the risk for hypotension, and to have adequate fluid intake.

Serious Urinary Tract Infections

Inform patients of the potential for urinary tract infections, which may be serious. Provide them with information on the symptoms of urinary tract infections. Advise them to seek medical advice promptly if such symptoms occur [see Warnings and Precautions (5.4)].

Hypoglycemia with Concomitant Use of Insulin or Insulin Secretagogues

Inform patients that the incidence of hypoglycemia may increase when XIGDUO XR is added to an insulin secretagogue (e.g., sulfonylurea) and/or insulin. Educate patients on the signs and symptoms of hypoglycemia [see Warnings and Precautions (5.5)].

Necrotizing Fasciitis of the Perineum (Fournier’s Gangrene)

Inform patients that necrotizing infections of the perineum (Fournier’s Gangrene) have occurred with dapagliflozin, a component of XIGDUO XR. Counsel patients to promptly seek medical attention if they develop pain or tenderness, redness, or swelling of the genitals or the area from the genitals back to the rectum, along with a fever above 100.4°F or malaise [see Warnings and Precautions (5.6)].

Genital Mycotic Infections in Females (e.g., Vulvovaginitis)

Inform female patients that vaginal yeast infections may occur and provide them with information on the signs and symptoms of vaginal yeast infections. Advise them of treatment options and when to seek medical advice [see Warnings and Precautions (5.8)].

Genital Mycotic Infections in Males (e.g., Balanitis or Balanoposthitis)

Inform male patients that yeast infections of the penis (e.g., balanitis or balanoposthitis) may occur, especially in patients with prior history. Provide them with information on the signs and symptoms of balanitis and balanoposthitis (rash or redness of the glans or foreskin of the penis). Advise them of treatment options and when to seek medical advice [see Warnings and Precautions (5.8)].

Hypersensitivity Reactions

Inform patients that serious hypersensitivity reactions (e.g., urticaria, anaphylactic reactions, and angioedema) have been reported with the components of XIGDUO XR. Advise patients to immediately report any signs or symptoms suggesting allergic reaction or angioedema, and to take no more of the drug until they have consulted prescribing physicians.

Pregnancy

Advise pregnant patients of the potential risk to a fetus with treatment with XIGDUO XR. Instruct patients to immediately inform their healthcare provider if pregnant or planning to become pregnant [see Use in Specific Populations (8.1)].

Lactation

Advise patients that use of XIGDUO XR is not recommended while breastfeeding [see Use in Specific Populations (8.2)].

Females and Males of Reproductive Potential

Inform female patients that treatment with metformin may result in an unintended pregnancy in some premenopausal anovulatory females due to its effect on ovulation [see Use in Specific Populations (8.3)].

Administration

Instruct patients that XIGDUO XR must be swallowed whole and not crushed or chewed, and that the inactive ingredients may occasionally be eliminated in the feces as a soft mass that may resemble the original tablet.

Laboratory Tests

Due to the mechanism of action of dapagliflozin, patients taking XIGDUO XR will test positive for glucose in their urine.

Missed Dose

If a dose is missed, advise patients to take it as soon as it is remembered unless it is almost time for the next dose, in which case patients should skip the missed dose and take the medicine at the next regularly scheduled time. Advise patients not to take two doses of XIGDUO XR at the same time.

FARXIGA® is a registered trademark of the AstraZeneca group of companies.

Distributed by:

AstraZeneca Pharmaceuticals LP

Wilmington, DE 19850

MEDICATION GUIDE

XIGDUO® XR [ZIG-DO-OH X-R]

(dapagliflozin and metformin hydrochloride extended-release)

tablets, for oral use

What is the most important information I should know about XIGDUO XR?

XIGDUO XR can cause serious side effects, including:

- Lactic Acidosis. Metformin, one of the medicines in XIGDUO XR, can cause a rare but serious condition called lactic acidosis (a build-up of an acid in the blood) that can cause death. Lactic acidosis is a medical emergency and must be treated in the hospital.

Stop taking XIGDUO XR and call your healthcare provider right away if you have any of the following symptoms, which could be signs of lactic acidosis:

  - you feel cold in your hands or feet
  - you feel dizzy or lightheaded
  - you have a slow or irregular heartbeat
  - you feel very weak or tired
  - you have unusual (not normal) muscle pain
  - you have trouble breathing
  - you feel unusual sleepiness or sleep longer than usual
  - you have stomach pains, nausea or vomiting

Most people who have had lactic acidosis with metformin have other things that, combined with the metformin use, led to the lactic acidosis. Tell your healthcare provider if you have any of the following, because you have a higher chance for getting lactic acidosis with XIGDUO XR if you:

  - have severe kidney problems or your kidneys are affected by certain x-ray tests that use injectable dye.
  - have liver problems.
  - drink alcohol very often or drink a lot of alcohol in the short-term ("binge" drinking).
  - get dehydrated (lose a large amount of body fluids). This can happen if you are sick with a fever, vomiting, or diarrhea. Dehydration can also happen when you sweat a lot with activity or exercise and do not drink enough fluids.
  - have surgery.
  - have new or worsening symptoms of congestive heart failure such as shortness of breath or increased fluid or swelling of the legs.
  - have a heart attack, severe infection, or stroke.
  - are 65 years of age or older.

The best way to keep from having a problem with lactic acidosis from metformin is to tell your healthcare provider if you have any of the problems in the list above. Your healthcare provider may decide to stop your XIGDUO XR for a while if you have any of these things.

- Diabetic Ketoacidosis (increased ketones in your blood or urine) in people with type 1 diabetes and other ketoacidosis. XIGDUO XR can cause ketoacidosis that can be life-threatening and may lead to death. Ketoacidosis is a serious condition which needs to be treated in a hospital. People with type 1 diabetes have a high risk of getting ketoacidosis. People with type 2 diabetes or pancreas problems also have an increased risk of getting ketoacidosis. Ketoacidosis can also happen in people who are sick, cannot eat or drink as usual, skip meals, are on a diet high in fat and low in carbohydrates (ketogenic diet), take less than the usual amount of insulin or miss insulin doses, drink too much alcohol, have a loss of too much fluid from the body (volume depletion), or who have surgery or a procedure that requires not having food for a long time (prolonged fasting). Ketoacidosis can happen even if your blood sugar is less than 250 mg/dL. Your healthcare provider may ask you to periodically check ketones in your urine or blood.
Stop taking XIGDUO XR and call your healthcare provider or get medical help right away if you get any of the following. If possible, check for ketones in your urine or blood, even if your blood sugar is less than 250 mg/dL.

- nausea
- vomiting
- stomach area (abdominal) pain

- tiredness
- trouble breathing
- ketones in your urine or blood

XIGDUO XR can have other serious side effects. See “What are the possible side effects of XIGDUO XR?”

What is XIGDUO XR?

- XIGDUO XR is a prescription medicine that contains 2 medicines called dapagliflozin (FARXIGA) and metformin HCl.
- XIGDUO XR can be used along with diet and exercise to improve blood sugar (glucose) in adults and children who are 10 years of age and older with type 2 diabetes.
- One of the medicines in XIGDUO XR, dapagliflozin (FARXIGA), can also be used in adults with type 2 diabetes who have:
  ∘ chronic kidney disease and dapagliflozin is needed to reduce the risk of further worsening of your kidney disease, end-stage kidney disease (ESKD), death due to cardiovascular disease, and hospitalization for heart failure.
  ∘ heart failure (when the heart cannot pump enough blood to the rest of your body) and dapagliflozin is needed to reduce the risk of cardiovascular death, hospitalization for heart failure and urgent heart failure visit.
  ∘ known cardiovascular disease or multiple cardiovascular risk factors and dapagliflozin is needed to reduce the risk of hospitalization for heart failure.
- XIGDUO XR is not for use to improve blood sugar (glucose) control in people with type 1 diabetes.
- XIGDUO XR is only for use in people with type 2 diabetes mellitus, because it contains the prescription medicine metformin HCl.
- XIGDUO XR is not for use for treatment of chronic kidney disease in people with certain genetic forms of polycystic kidney disease, or who are taking or have recently received immunosuppressive therapy to treat kidney disease. If you have these conditions, XIGDUO XR is not expected to work for treatment of chronic kidney disease.
- It is not known if XIGDUO XR is safe and effective to lower blood sugar (glucose) in children younger than 10 years of age with type 2 diabetes mellitus.
- It is not known if XIGDUO XR is safe and effective for treatment of heart failure or chronic kidney disease in children younger than 18 years of age.

Who should not take XIGDUO XR?

Do not take XIGDUO XR if you:

- have severe kidney problems.
- are allergic to dapagliflozin, metformin HCl, or any of the ingredients in XIGDUO XR. See the end of this Medication Guide for a complete list of ingredients in XIGDUO XR. Symptoms of a serious allergic reaction to XIGDUO XR may include:
  - rash
  - raised red patches on your skin (hives)
  - swelling of the face, lips, tongue, and throat that may cause difficulty in breathing or swallowing.
If you have any of these symptoms, stop taking XIGDUO XR and contact your healthcare provider or go to the nearest hospital emergency room right away.
- have a condition called metabolic acidosis or diabetic ketoacidosis (increased ketones in your blood or urine).

What should I tell my healthcare provider before taking XIGDUO XR?

Before you take XIGDUO XR, tell your healthcare provider if you:

- have type 1 diabetes or have had diabetic ketoacidosis.
- have a decrease in your insulin dose.
- have a serious infection.
- have a history of infection of the vagina or penis.
- have kidney problems.
- have liver problems.
- have a history of urinary tract infections or problems with urination.
- are on a low sodium (salt) diet. Your healthcare provider may ask you to change your diet.
- have heart problems, including congestive heart failure.
- are 65 years of age or older.
- are going to have surgery or a procedure that requires not having food for a long time (prolonged fasting). Your healthcare provider may stop XIGDUO XR before you have surgery. Talk to your healthcare provider if you are having surgery about when to stop taking XIGDUO XR and when to start it again.
- are eating less, or there is a change in your diet.
- are dehydrated.
- have or have had problems with your pancreas, including pancreatitis or surgery on your pancreas.
- drink alcohol very often or drink a lot of alcohol in the short-term (“binge” drinking).
- are going to get an injection of dye or contrast agents for an x-ray procedure. XIGDUO XR may need to be stopped for a short time. Talk to your healthcare provider about when you should stop XIGDUO XR and when you should start XIGDUO XR again. See “What is the most important information I should know about XIGDUO XR?”
- have low levels of vitamin B12 in your blood.
- are pregnant or plan to become pregnant. XIGDUO XR may harm your unborn baby. If you are pregnant or plan to become pregnant, talk to your healthcare provider about the best way to control your blood sugar.
- are breastfeeding or plan to breastfeed. It is not known if XIGDUO XR passes into your breast milk. Talk with your healthcare provider about the best way to feed your baby if you are taking XIGDUO XR. You should not breastfeed if you take XIGDUO XR.
- are a person who has not gone through menopause (premenopausal) who does not have periods regularly or at all. XIGDUO XR can cause the release of an egg from an ovary in a person (ovulation). This can increase your chance of getting pregnant. Tell your healthcare provider right away if you become pregnant while taking XIGDUO XR.

Tell your healthcare provider about all the medicines you take, including prescription and over-the-counter medicines, vitamins, and herbal supplements.

XIGDUO XR may affect the way other medicines work and other medicines may affect the way XIGDUO XR works.

Know the medicines you take. Keep a list of them and show it to your healthcare provider and pharmacist when you get a new medicine.

How should I take XIGDUO XR?

- Take XIGDUO XR exactly as your healthcare provider tells you to take it.
- Your healthcare provider will tell you how much XIGDUO XR to take and when to take it. Your healthcare provider may change your dose if needed.
- Take XIGDUO XR by mouth 1 time each day with meals to lower your chance of an upset stomach. Talk to your healthcare provider about the best time of day for you.
- Swallow XIGDUO XR whole. Do not crush, cut, or chew XIGDUO XR.
- You may sometimes pass a soft mass in your stools (bowel movement) that looks like XIGDUO XR tablets.
- If you miss a dose of XIGDUO XR, take it as soon as you remember. If it is almost time for your next dose, skip the missed dose and take the medicine at the next regularly scheduled time. Do not take 2 doses of XIGDUO XR at the same time. Talk with your healthcare provider if you have questions about a missed dose.
- If you take too much XIGDUO XR, call your healthcare provider or Poison Help line at 1-800-222-1222, or go to the nearest hospital emergency room right away.
- When your body is under some types of stress, such as fever, trauma (such as a car accident), infection, or surgery, the amount of diabetes medicine you need may change. Tell your healthcare provider right away if you have any of these conditions and follow your healthcare provider’s instructions.
- Your healthcare provider may tell you to stop taking XIGDUO XR at least 3 days before any surgery or procedure that requires not having food or water for a long time (prolonged fasting).
- Your healthcare provider may tell you to take XIGDUO XR along with other diabetes medicines. Low blood sugar can happen more often when XIGDUO XR is taken with certain other diabetes medicines. See “What are the possible side effects of XIGUDO XR?”.
- XIGDUO XR will cause your urine to test positive for glucose.
- Your healthcare provider may do certain blood tests before you start XIGDUO XR and during treatment as needed. Your healthcare provider may change your dose of XIGDUO XR based on the results of your blood tests.

What should I avoid while taking XIGDUO XR?

- Avoid drinking alcohol very often or drinking a lot of alcohol in a short period of time (“binge” drinking). It can increase your chances of getting serious side effects.

What are the possible side effects of XIGDUO XR?

XIGDUO XR may cause serious side effects including:

See “What is the most important information I should know about XIGDUO XR?”.

- Dehydration. XIGDUO XR can cause some people to become dehydrated (the loss of body water and salt). Dehydration may cause you to feel dizzy, faint, lightheaded, or weak, especially when you stand up (orthostatic hypotension). There have been reports of sudden kidney injury in people with type 2 diabetes mellitus who are taking dapagliflozin, a medicine in XIGDUO XR.
You may be at a higher risk of dehydration if you:
  1. take medicines to lower your blood pressure, including water pills (diuretics)
  2. are on a low salt diet
  3. have kidney problems
  4. are 65 years of age or older
Talk to your healthcare provider about what you can do to prevent dehydration including how much fluid you should drink on a daily basis. Call your healthcare provider right away if you reduce the amount of food or liquid you drink, for example if you cannot eat or you start to lose liquids from your body, for example from vomiting, diarrhea, or being in the sun too long.
- Serious urinary tract infections. Serious urinary tract infections that may lead to hospitalization have happened in people who are taking dapagliflozin, one of the medicines in XIGDUO XR. Tell your healthcare provider if you have any signs or symptoms of a urinary tract infection, such as a burning feeling when passing urine, a need to urinate often, the need to urinate right away, pain in the lower part of your stomach (pelvis), or blood in the urine. Sometimes people also may have a fever, back pain, nausea or vomiting.
- Low blood sugar (hypoglycemia). If you take XIGDUO XR with another medicine that can cause low blood sugar, such as sulfonylureas or insulin, your risk of getting low blood sugar is higher. The dose of your sulfonylurea medicine or insulin may need to be lowered while you take XIGDUO XR. Signs and symptoms of low blood sugar may include:

- headache
- confusion
- hunger
- shaking or feeling jittery

- drowsiness
- dizziness
- fast heartbeat

- weakness
- sweating
- irritability

- A rare but serious bacterial infection that causes damage to the tissue under the skin (necrotizing fasciitis) in the area between and around the anus and genitals (perineum). Necrotizing fasciitis of the perineum has happened in women and men who take dapagliflozin, one of the medicines in XIGDUO XR. Necrotizing fasciitis of the perineum may lead to hospitalization, may require multiple surgeries and may lead to death. Seek medical attention right away if you have a fever or you are feeling very weak, tired or uncomfortable (malaise) and you develop any of the following symptoms in the area between and around the anus and genitals:

- pain or tenderness

- swelling

- redness of skin
  (erythema)

- Serious allergic reaction. If you have any symptoms of a serious allergic reaction, stop taking XIGDUO XR and call your healthcare provider right away or go to the nearest hospital emergency room. See “Who should not take XIGDUO XR?”. Your healthcare provider may give you a medicine for your allergic reaction and prescribe a different medicine for your diabetes.
- Low vitamin B12 (vitamin B12 deficiency). Using metformin for long periods of time may cause a decrease in the amount of vitamin B12 in your blood, especially if you have had low vitamin B12 levels before. Your healthcare provider may do blood tests to check your vitamin B12 levels.
- Vaginal yeast infection. Women who take XIGDUO XR may get vaginal yeast infections. Symptoms of a vaginal yeast infection include:
  - vaginal odor
  - white or yellowish vaginal discharge (discharge may be lumpy or look like cottage cheese)
  - vaginal itching
- Yeast infection of the penis (balanitis). Men who take XIGDUO XR may get a yeast infection of the skin around the penis. Men who are not circumcised may have swelling of the penis that makes it difficult to pull back the skin around the tip of the penis. Other symptoms of a yeast infection of the penis include:
  - redness, itching, or swelling of the penis
  - foul smelling discharge from the penis
  - rash of the penis
  - pain in the skin around the penis
  Talk to your healthcare provider about what to do if you get symptoms of a yeast infection of the vagina or penis. Your healthcare provider may suggest you use an over-the-counter antifungal medicine. Talk to your healthcare provider right away if you use an over-the-counter antifungal medicine and your symptoms do not go away.

The most common side effects of XIGDUO XR include:

    - vaginal yeast infections
    - diarrhea
    - headache

∘ stuffy or runny nose and sore throat
∘ urinary tract infection

Tell your healthcare provider or pharmacist if you have any side effect that bothers you or does not go away.

These are not all of the possible side effects of XIGDUO XR. For more information, ask your healthcare provider or pharmacist.

Call your doctor for medical advice about side effects. You may report side effects to FDA at 1-800-FDA-1088.

How should I store XIGDUO XR?

Store XIGDUO XR at room temperature between 68°F and 77°F (20°C and 25°C).

Keep XIGDUO XR and all medicines out of the reach of children.

General information about the safe and effective use of XIGDUO XR.

Medicines are sometimes prescribed for purposes other than those listed in a Medication Guide. Do not use XIGDUO XR for a condition for which it is not prescribed. Do not give XIGDUO XR to other people, even if they have the same symptoms you have. It may harm them.

This Medication Guide summarizes the most important information about XIGDUO XR. If you would like more information, talk to your healthcare provider. You can ask your pharmacist or healthcare provider for information about XIGDUO XR that is written for health professionals.

For more information, go to www.xigduoxr.com or call 1-800-236-9933

What are the ingredients in XIGDUO XR?

Active ingredients: dapagliflozin and metformin hydrochloride

Inactive ingredients: anhydrous lactose, carboxymethylcellulose sodium, crospovidone, hypromellose, magnesium stearate, microcrystalline cellulose, and silicon dioxide.

The film coatings contain the following inactive ingredients: polyethylene glycol, polyvinyl alcohol, talc, and titanium dioxide. Additionally, the film coating for the XIGDUO XR 5 mg/500 mg tablets contains FD&C Yellow No. 6/Sunset Yellow FCF aluminum lake and the film coating for the XIGDUO XR 2.5 mg/1000 mg, 5 mg/1000 mg, 10 mg/500 mg, and 10 mg/1000 mg tablets contains iron oxides.

Distributed by: AstraZeneca Pharmaceuticals LP Wilmington, DE 19850

This Medication Guide has been approved by the U.S. Food and Drug Administration. Revised: 12/2024

PACKAGE/LABEL PRINCIPAL DISPLAY PANEL – 2.5 mg/1000 mg

60 Tablets NDC 0310-6225-60

xigduo® XR

(dapagliflozin/metformin HCl

extended-release) tablets

2.5 mg/1000 mg

Dispense with Medication Guide

Rx only

Do not crush, cut, or chew tablets.

Tablets must be swallowed whole.

AstraZeneca

PACKAGE/LABEL PRINCIPAL DISPLAY PANEL – 5 mg/500 mg

30 Tablets NDC 0310-6250-30

xigduo® XR

(dapagliflozin/metformin HCl

extended-release) tablets

5 mg/500 mg

Dispense with Medication Guide

Rx only

Do not crush, cut, or chew tablets.

Tablets must be swallowed whole.

AstraZeneca

PACKAGE/LABEL PRINCIPAL DISPLAY PANEL – 5 mg/1000 mg

60 Tablets NDC 0310-6260-60

xigduo® XR

(dapagliflozin/metformin HCl

extended-release) tablets

5 mg/1000 mg

Dispense with Medication Guide

Rx only

Do not crush, cut, or chew tablets.

Tablets must be swallowed whole.

AstraZeneca

PACKAGE/LABEL PRINCIPAL DISPLAY PANEL – 10 mg/500 mg

30 Tablets NDC 0310-6270-30

xigduo® XR

(dapagliflozin/metformin HCl

extended-release) tablets

10 mg/500 mg

Dispense with Medication Guide

Rx only

Do not crush, cut, or chew tablets.

Tablets must be swallowed whole.

AstraZeneca

PACKAGE/LABEL PRINCIPAL DISPLAY PANEL – 10 mg/1000 mg

30 Tablets NDC 0310-6280-30

xigduo® XR

(dapagliflozin/metformin HCl

extended-release) tablets

10 mg/1000 mg

Dispense with Medication Guide

Rx only

Do not crush, cut, or chew tablets.

Tablets must be swallowed whole.

AstraZeneca